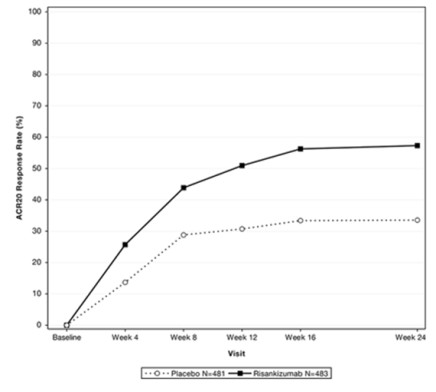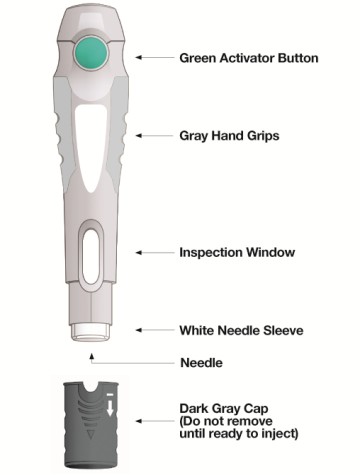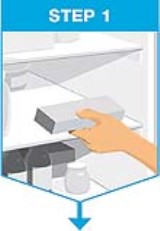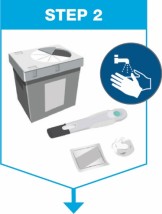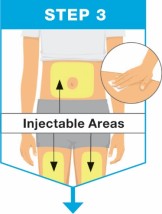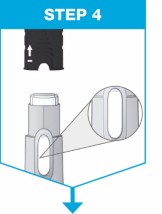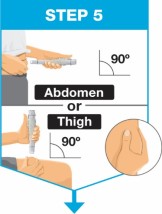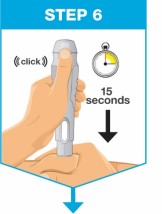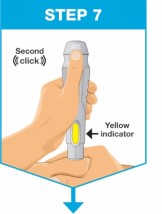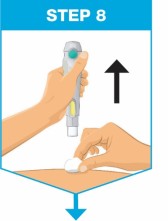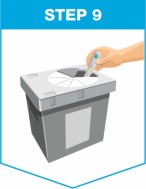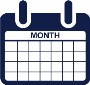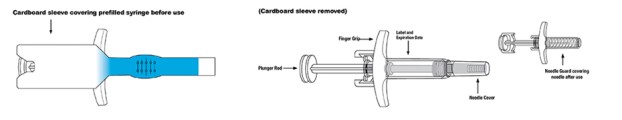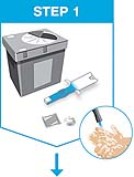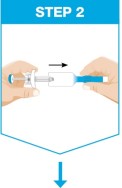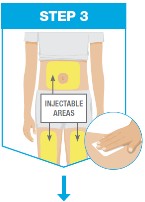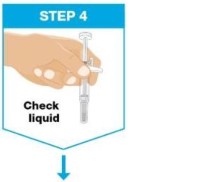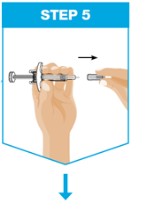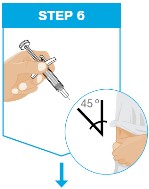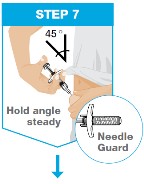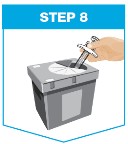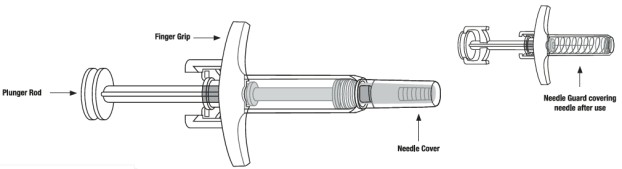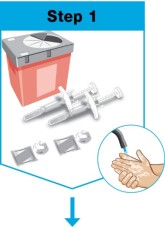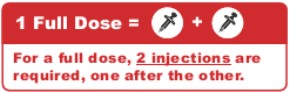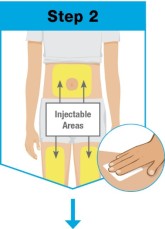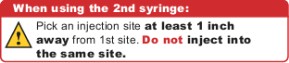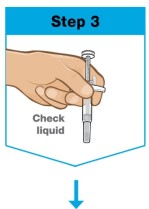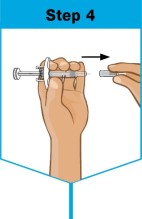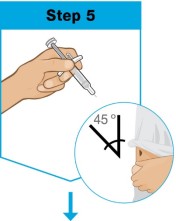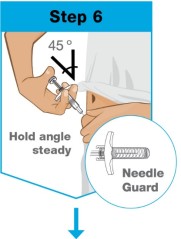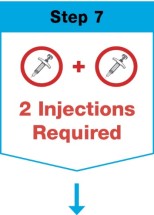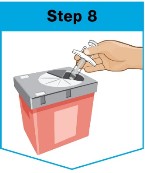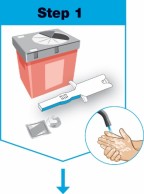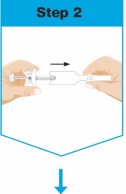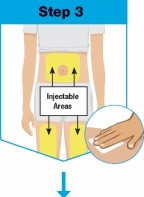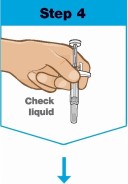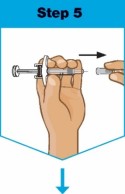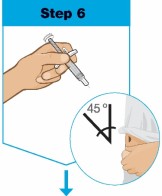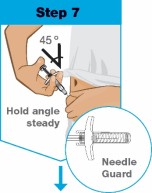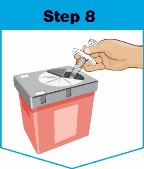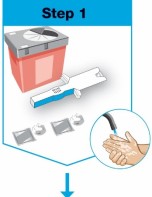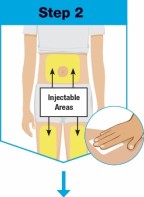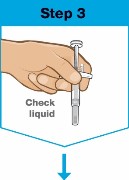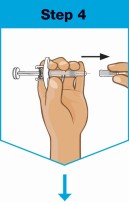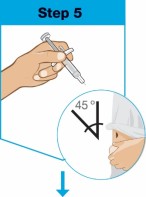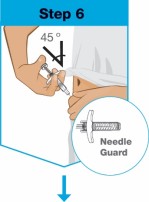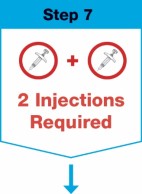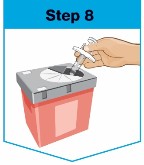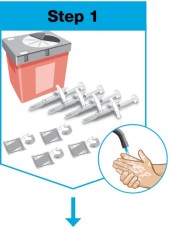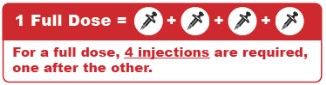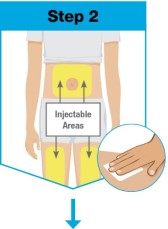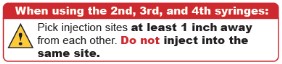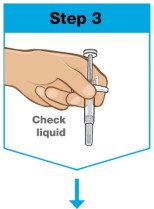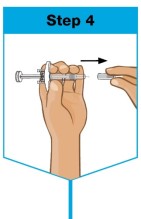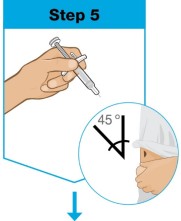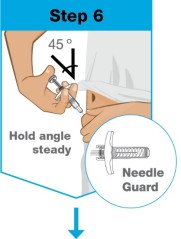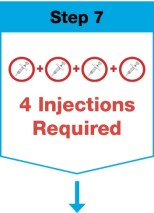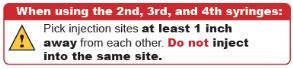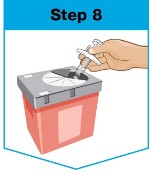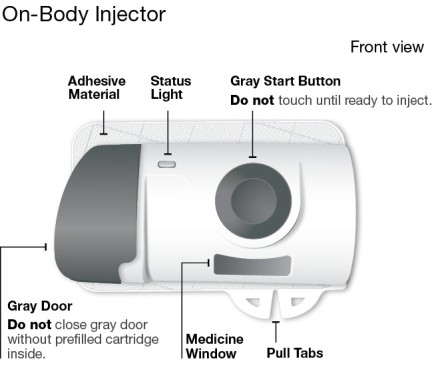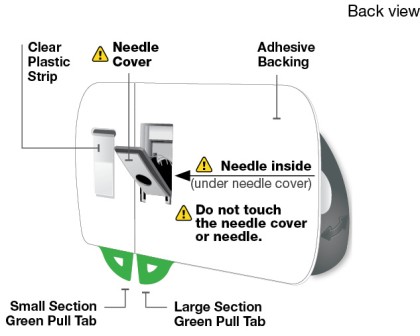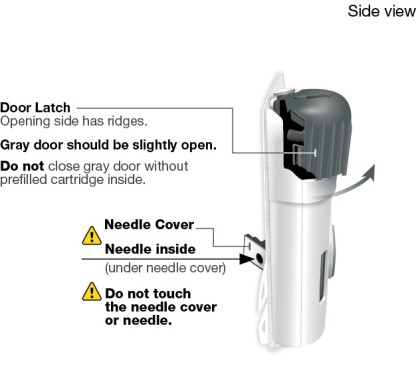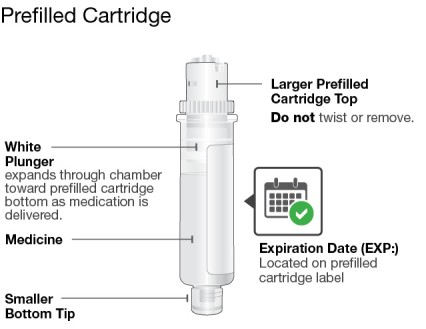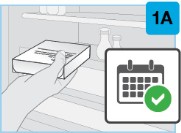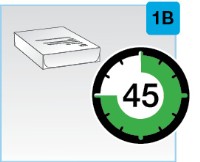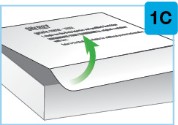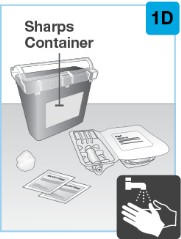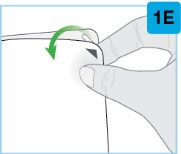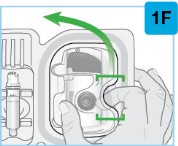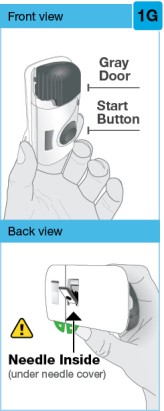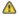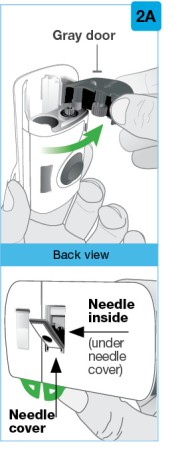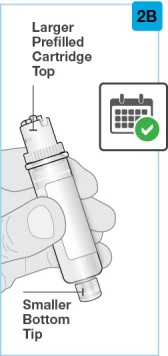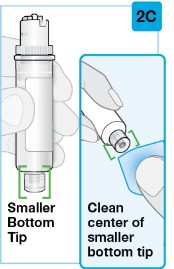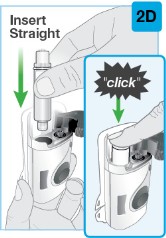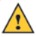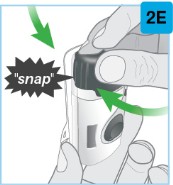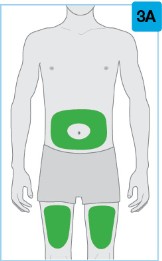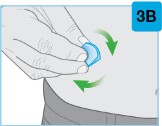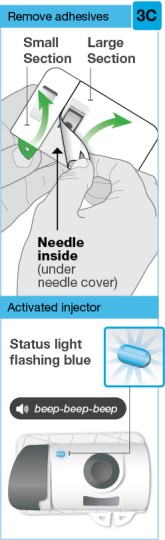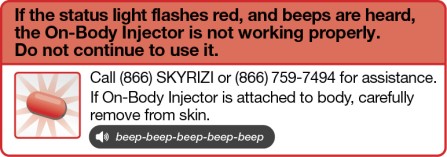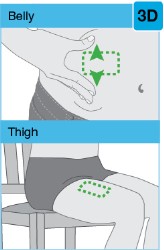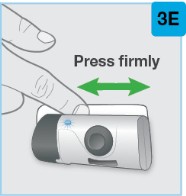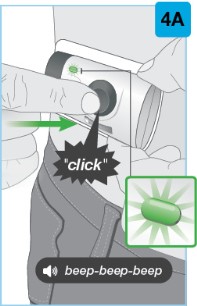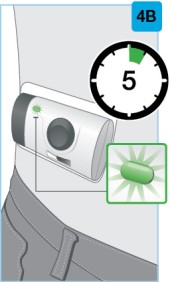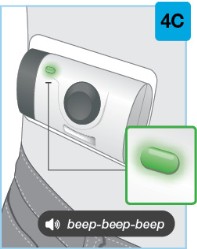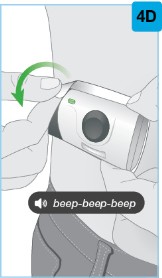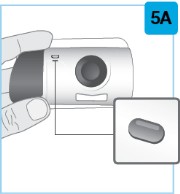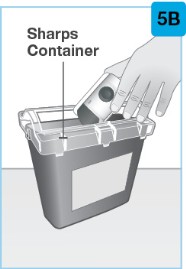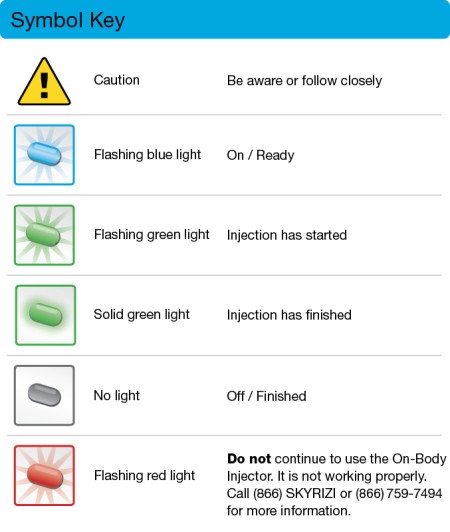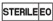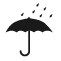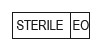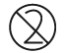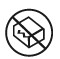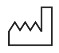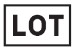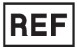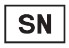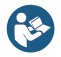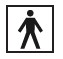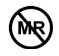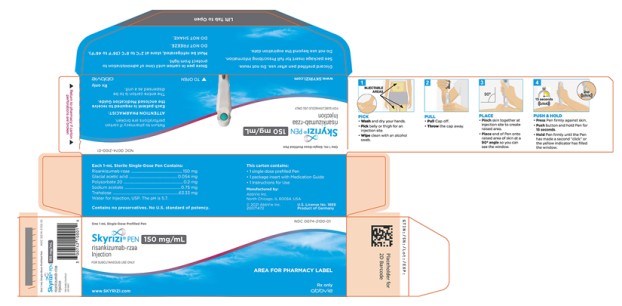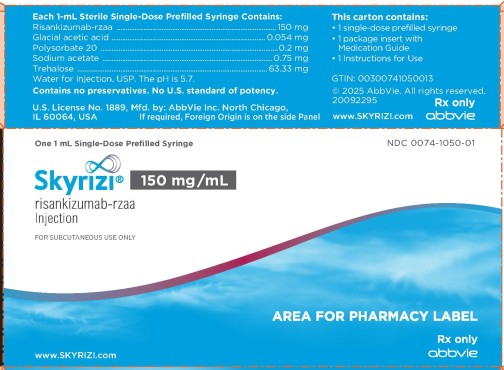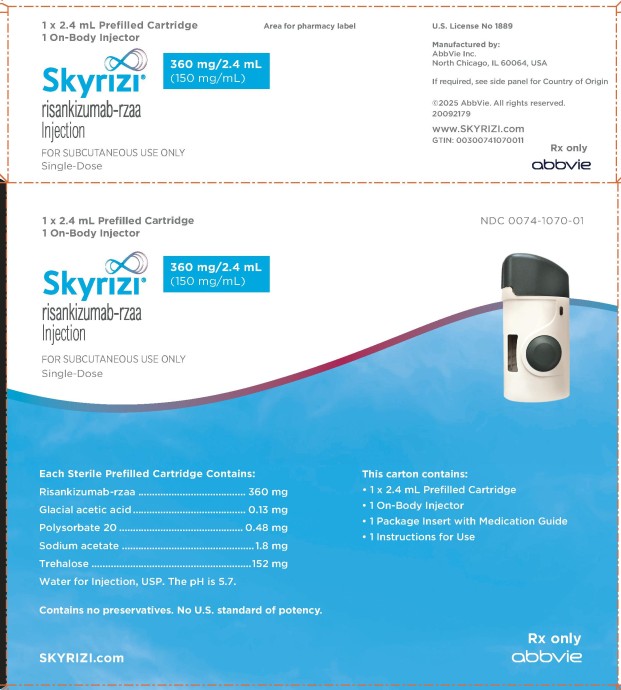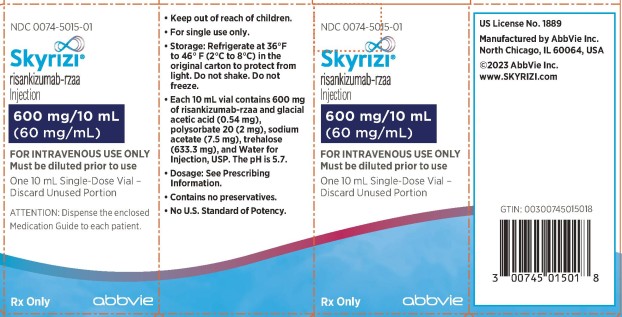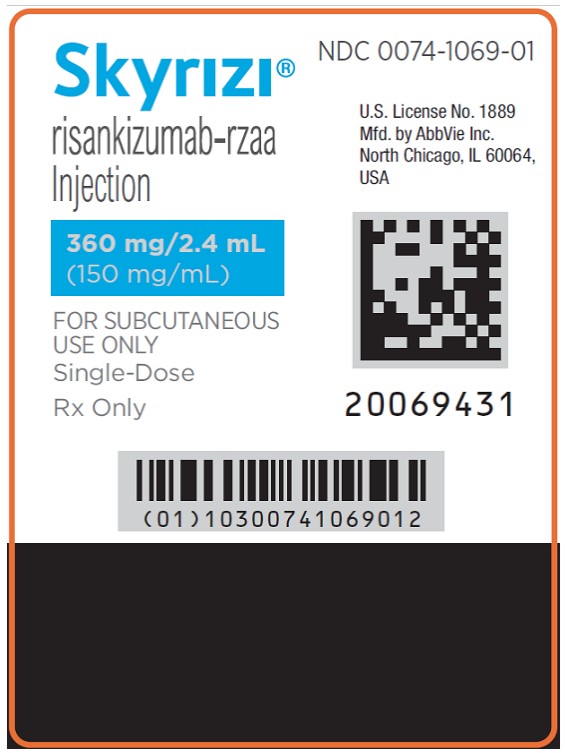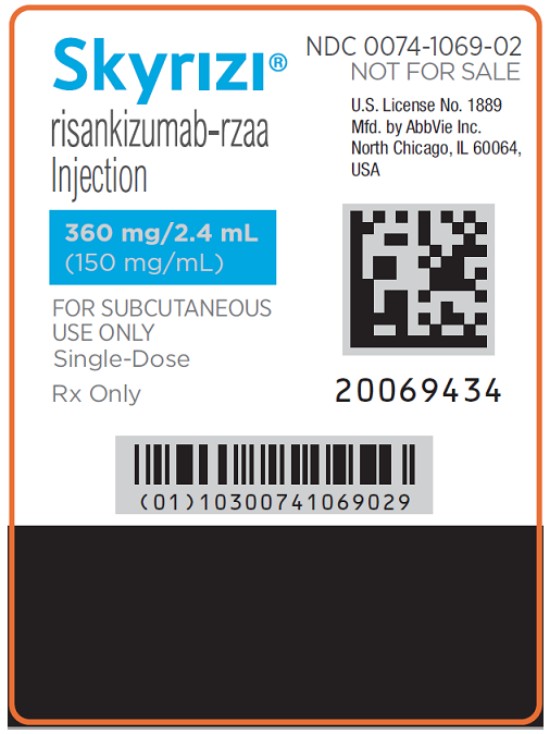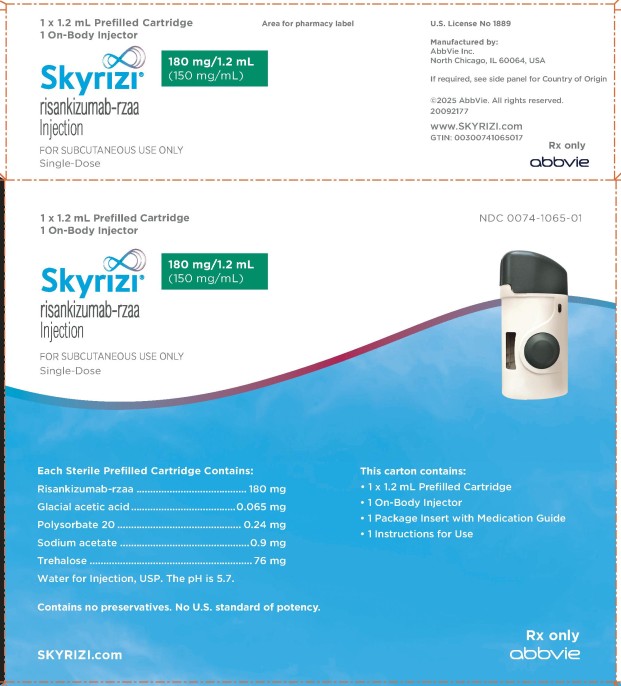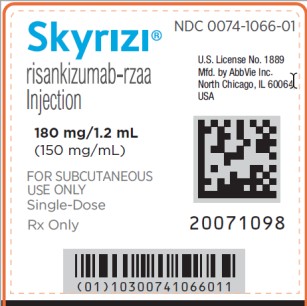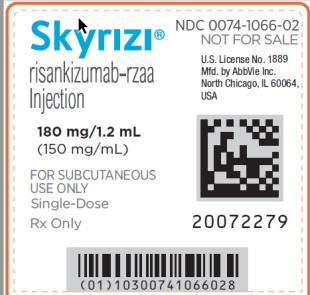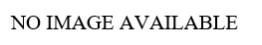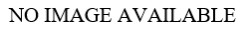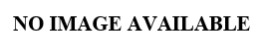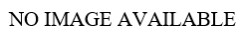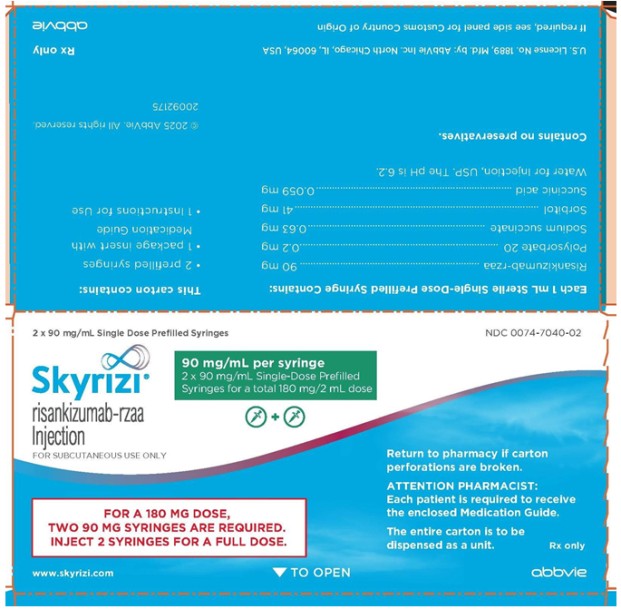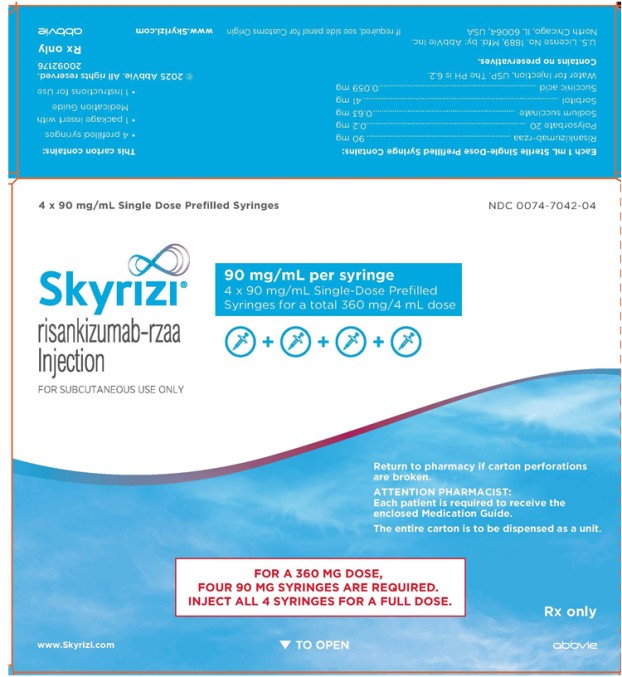 DRUG LABEL: Skyrizi
NDC: 0074-2042 | Form: KIT | Route: SUBCUTANEOUS
Manufacturer: AbbVie Inc.
Category: prescription | Type: HUMAN PRESCRIPTION DRUG LABEL
Date: 20250903

ACTIVE INGREDIENTS: RISANKIZUMAB 75 mg/0.83 mL; ISOPROPYL ALCOHOL 0.70 mL/1 mL
INACTIVE INGREDIENTS: SUCCINIC ACID 0.049 mg/0.83 mL; SORBITOL 34 mg/0.83 mL; POLYSORBATE 20 0.17 mg/0.83 mL; WATER; SODIUM SUCCINATE ANHYDROUS 0.53 mg/0.83 mL; WATER

HIGHLIGHTS OF PRESCRIBING INFORMATION

These highlights do not include all the information needed to use SKYRIZI safely and effectively. See full prescribing information for SKYRIZI.
SKYRIZI® (risankizumab-rzaa) injection, for subcutaneous or intravenous use
Initial U.S. Approval: 2019

RECENT MAJOR CHANGES

Dosage and Administration, General Considerations for Administration (2.2) | 9/2025
Dosage and Administration, Preparation and Administration Instructions (Crohn’s Disease and Ulcerative Colitis) (2.8) | 9/2025

1 INDICATIONS AND USAGE

SKYRIZI is an interleukin-23 antagonist indicated for the treatment of:

- moderate-to-severe plaque psoriasis in adults who are candidates for systemic therapy or phototherapy. (1.1)
- active psoriatic arthritis in adults. (1.2)
- moderately to severely active Crohn's disease in adults. (1.3)
- moderately to severely active ulcerative colitis in adults. (1.4)

2 DOSAGE AND ADMINISTRATION

- For the treatment of Crohn’s disease and ulcerative colitis: Obtain liver enzymes and bilirubin levels prior to initiating treatment with SKYRIZI. (2.1, 5.4)
- Complete all age-appropriate vaccinations as recommended by current immunization guidelines (2.1, 5.5)

Recommended Dosage

Plaque Psoriasis and Psoriatic Arthritis:

- 150 mg administered by subcutaneous injection at Week 0, Week 4, and every 12 weeks thereafter. (2.3, 2.4)
- In patients with psoriatic arthritis SKYRIZI can be administered alone or in combination with non-biologic disease-modifying antirheumatic drugs (DMARDs). (2.4)

Crohn’s Disease:

- The recommended induction dosage is 600 mg administered by intravenous infusion over at least one hour at Week 0, Week 4, and Week 8. The recommended maintenance dosage is 180 mg or 360 mg administered by subcutaneous injection at Week 12, and every 8 weeks thereafter. Use the lowest effective dosage to maintain therapeutic response. (2.6)

Ulcerative Colitis:

- The recommended induction dosage is 1,200 mg administered by intravenous infusion over at least two hours at Week 0, Week 4, and Week 8. The recommended maintenance dosage is 180 mg or 360 mg administered by subcutaneous injection at Week 12, and every 8 weeks thereafter. Use the lowest effective dosage to maintain therapeutic response. (2.7)

3 DOSAGE FORMS AND STRENGTHS

Subcutaneous injection (3)

- Injection: 150 mg/mL in each single-dose prefilled pen.
- Injection: 90 mg/mL in each single-dose prefilled syringe.
- Injection: 150 mg/mL in each single-dose prefilled syringe.
- Injection: 180 mg/1.2 mL (150 mg/mL) in each single-dose prefilled syringe.
- Injection: 180 mg/1.2 mL (150 mg/mL) in each single-dose prefilled cartridge.
- Injection: 360 mg/2.4 mL (150 mg/mL) in each single-dose prefilled cartridge.

Intravenous infusion (3)

- Injection: 600 mg/10 mL (60 mg/mL) in each single-dose vial.

4 CONTRAINDICATIONS

- SKYRIZI is contraindicated in patients with a history of serious hypersensitivity reaction to risankizumab-rzaa or any of the excipients (4)

5 WARNINGS AND PRECAUTIONS

- Hypersensitivity Reactions: Serious hypersensitivity reactions, including anaphylaxis, may occur. (5.1)
- Infections: SKYRIZI may increase the risk of infection. Instruct patients to seek medical advice if signs or symptoms of clinically important infection occur. If such an infection develops, do not administer SKYRIZI until the infection resolves. (5.2)
- Tuberculosis (TB): Evaluate for TB prior to initiating treatment with SKYRIZI. (5.3)
- Hepatotoxicity in Treatment of Inflammatory Bowel Disease: Drug-induced liver injury during induction has been reported. Monitor liver enzymes and bilirubin levels at baseline and, during induction, up to at least 12 weeks of treatment. Monitor thereafter according to routine patient management. (5.4)
- Administration of Vaccines: Avoid use of live vaccines. (5.5)

6 ADVERSE REACTIONS

Most common adverse reactions are:

- Plaque Psoriasis and Psoriatic Arthritis (≥ 1%): upper respiratory infections, headache, fatigue, injection site reactions, and tinea infections. (6.1)
- Crohn’s Disease (>3%):
  ◦ Induction: upper respiratory infections, headache, and arthralgia. (6.1)
  ◦ Maintenance: arthralgia, abdominal pain, injection site reactions, anemia, pyrexia, back pain, arthropathy, and urinary tract infection. (6.1)
- Ulcerative Colitis (≥3%):
  ◦ Induction: arthralgia. (6.1)
  ◦ Maintenance: arthralgia, pyrexia, injection site reactions, and rash. (6.1)

To report SUSPECTED ADVERSE REACTIONS, contact AbbVie Inc. at 1-800-633-9110 or FDA at 1-800-FDA-1088 or www.fda.gov/medwatch.

FULL PRESCRIBING INFORMATION

1 INDICATIONS AND USAGE

1.1 Plaque Psoriasis

SKYRIZI® is indicated for the treatment of moderate-to-severe plaque psoriasis in adults who are candidates for systemic therapy or phototherapy.

1.2 Psoriatic Arthritis

SKYRIZI is indicated for the treatment of active psoriatic arthritis in adults.

1.3 Crohn’s Disease

SKYRIZI is indicated for the treatment of moderately to severely active Crohn's disease in adults.

1.4 Ulcerative Colitis

SKYRIZI is indicated for the treatment of moderately to severely active ulcerative colitis in adults.

2 DOSAGE AND ADMINISTRATION

2.1 Procedures Prior to Treatment Initiation

- For the treatment of Crohn’s disease and ulcerative colitis, obtain liver enzymes and bilirubin levels prior to initiating treatment with SKYRIZI [see Warnings and Precautions (5.4)]
- Evaluate patients for tuberculosis (TB) infection prior to initiating treatment with SKYRIZI [see Warnings and Precautions (5.3)].
- Complete all age-appropriate vaccinations as recommended by current immunization guidelines [see Warnings and Precautions (5.5)].

2.2 General Considerations for Administration

• Visually inspect SKYRIZI for particulate matter and discoloration prior to administration. The solution may contain a few translucent to white particles.

○ SKYRIZI 150 mg/mL prefilled pen or prefilled syringe, 180 mg/1.2 mL prefilled syringe or prefilled cartridge, and 360 mg/2.4 mL prefilled cartridge: a colorless to yellow, and clear to slightly opalescent solution.

○ SKYRIZI 90 mg/mL prefilled syringe and 600 mg/10 mL vial: a colorless to slightly yellow, and clear to slightly opalescent solution.

○ Do not use if the solution contains large particles or is cloudy or discolored.

• Discard after use. Do not reuse.

2.3 Recommended Dosage for Plaque Psoriasis

The recommended dosage is 150 mg administered by subcutaneous injection at Week 0, Week 4, and every 12 weeks thereafter.

2.4 Recommended Dosage for Psoriatic Arthritis

The recommended dosage is 150 mg administered by subcutaneous injection at Week 0, Week 4, and every 12 weeks thereafter.

SKYRIZI may be administered alone or in combination with non-biologic disease-modifying antirheumatic drugs (DMARDs).

2.5 Preparation and Administration Instructions (Plaque Psoriasis and Psoriatic Arthritis)

- Administer SKYRIZI 150 mg/mL prefilled pen or prefilled syringe subcutaneously.
- Patients may self-inject SKYRIZI after training in subcutaneous injection technique. Provide proper training to patients and/or caregivers on the subcutaneous injection technique of SKYRIZI.
- Before injecting, remove the carton with SKYRIZI from the refrigerator and without removing the prefilled pen or prefilled syringe from the carton, allow SKYRIZI to reach room temperature out of direct sunlight (30 to 90 minutes for the prefilled pen and 15 to 30 minutes for the prefilled syringe).
- Do not inject into areas where the skin is tender, bruised, erythematous, indurated or affected by psoriasis. Administration of SKYRIZI in the upper, outer arm may only be performed by a healthcare professional or caregiver.
- If a dose is missed, administer the dose as soon as possible. Thereafter, resume dosing at the regular scheduled time.

The SKYRIZI “Instructions for Use” contains more detailed instructions on the preparation and administration of SKYRIZI [see Instructions for Use]. Instruct the patient to read the Instructions for Use before administration.

2.6 Recommended Dosage for Crohn’s Disease

Adult Patients: Induction

The recommended induction dosage of SKYRIZI is 600 mg administered by intravenous infusion over a period of at least one hour at Week 0, Week 4, and Week 8.

Adult Patients: Maintenance

The recommended maintenance dosage of SKYRIZI is 180 mg or 360 mg administered by subcutaneous injection at Week 12, and every 8 weeks thereafter. Use the lowest effective dosage needed to maintain therapeutic response.

2.7 Recommended Dosage for Ulcerative Colitis

Adult Patients: Induction

The recommended induction dosage of SKYRIZI is 1,200 mg administered by intravenous infusion over a period of at least two hours at Week 0, Week 4, and Week 8.

Adult Patients: Maintenance

The recommended maintenance dosage of SKYRIZI is 180 mg or 360 mg administered by subcutaneous injection at Week 12, and every 8 weeks thereafter. Use the lowest effective dosage needed to maintain therapeutic response.

2.8 Preparation and Administration Instructions (Crohn’s Disease and Ulcerative Colitis)

Intravenous Induction Dosing Regimen:

1. SKYRIZI vial for intravenous administration is intended for administration by a healthcare provider using aseptic technique.

2. Prior to intravenous administration, determine the dose and number of SKYRIZI vials needed based on the patient’s indication (see table below). Withdraw 10 mL of SKYRIZI solution from a vial (600 mg/10 mL) and inject into an intravenous infusion bag or glass bottle containing 5% Dextrose Injection or 0.9% Sodium Chloride Injection (see Table 1 below) for a final concentration of approximately 1.2 mg/mL to 6 mg/mL. Discard any remaining solution in the vial.

Table 1. Total Volume of Diluent Required for Intravenous Induction Dose
Indication | Intravenous Induction Dose | Number of SKYRIZI 600 mg/10 mL Vials | Total Volume of 5% Dextrose or 0.9% Sodium Chloride Injection
Crohn’s disease | 600 mg | 1 | 100 mL, or 250 mL, or 500 mL
Ulcerative colitis | 1,200 mg | 2 | 250 mL, or 500 mL

3. Infuse the diluted solution intravenously over a period of at least one hour for the SKYRIZI 600 mg dose; at least two hours for the SKYRIZI 1,200 mg dose. If stored refrigerated, allow the diluted SKYRIZI solution in the infusion bag or glass bottle to warm to room temperature prior to the start of the intravenous infusion.

4. Do not administer SKYRIZI diluted solution concomitantly in the same intravenous line with other medicinal products.

Handling and Storage of the Vial and the Diluted Solution:

- Do not shake the vial or diluted solution in the infusion bag or glass bottle.
- Use the prepared infusion immediately. If not used immediately, store the diluted SKYRIZI solution refrigerated and protected from light for up to 20 hours between 36°F to 46°F (2°C to 8°C).
- Immediately after preparation or removal from refrigeration, the diluted SKYRIZI solution can be stored at room temperature at up to 77°F (25°C) (protected from sunlight) for up to 8 hours. Storage time at room temperature begins once the diluted solution has been prepared. The infusion should be completed within 8 hours after dilution in the infusion bag.
- Exposure to indoor light is acceptable during room temperature storage and administration.
- Do not freeze.

Subcutaneous Maintenance Dosing Regimen:

Using the single-dose 180 mg or 360 mg prefilled cartridge with On-Body Injector:

- SKYRIZI is intended for use under the guidance and supervision of a healthcare professional.
- Patients may self-inject SKYRIZI using the on-body injector with prefilled cartridge after training in subcutaneous injection technique. Provide proper training to patients and/or caregivers on the subcutaneous injection technique of SKYRIZI.
- Before using the on-body injector with prefilled cartridge, remove the carton from the refrigerator and allow to reach room temperature out of direct sunlight (45 to 90 minutes) without removing the prefilled cartridge or on-body injector from the carton.
- Use the on-body injector to administer SKYRIZI 180 mg/1.2 mL or SKYRIZI 360 mg/2.4 mL prefilled cartridge subcutaneously on thigh or abdomen.
- Start the injection within 5 minutes after inserting the prefilled cartridge into the On-Body Injector.
- Do not inject into areas where the skin is tender, bruised, erythematous, indurated or affected by any lesions.
- If a dose is missed, administer the dose as soon as possible. Thereafter, resume dosing at the regular scheduled time.

The SKYRIZI “Instructions for Use” contains more detailed instructions on the preparation and administration of SKYRIZI [see Instructions for Use]. Instruct the patient to read the Instructions for Use before administration.

Using the 90 mg/mL or 180 mg/1.2 mL prefilled syringe:

• Administer each SKYRIZI 90 mg/mL or 180 mg/1.2 mL prefilled syringe subcutaneously.

• Patients may self-inject SKYRIZI after training in subcutaneous injection technique. Provide proper training to patients and/or caregivers on the subcutaneous injection technique of SKYRIZI.

• Before injecting, remove the carton from the refrigerator and without removing the prefilled syringes from the carton, allow SKYRIZI to reach room temperature out of direct sunlight (15 to 30 minutes).

• Use the 90 mg/mL or 180 mg/1.2 mL prefilled syringe(s) to administer SKYRIZI 180 mg or SKYRIZI 360 mg subcutaneously as follows:

○ 180 mg maintenance dose:

▪ SKYRIZI 90 mg/mL prefilled syringes: Two 90 mg prefilled syringes are required. Inject one prefilled syringe after the other in different anatomic locations (such as thighs or abdomen).

▪ SKYRIZI 180 mg/1.2 mL prefilled syringe: One 180 mg prefilled syringe is required.

○ 360 mg maintenance dose:

▪ SKYRIZI 90 mg/mL prefilled syringes: Four 90 mg prefilled syringes are required. Inject one prefilled syringe after the other in different anatomic locations (such as thighs or abdomen).

▪ SKYRIZI 180 mg/1.2 mL prefilled syringes: Two 180 mg prefilled syringes are required. Inject one prefilled syringe after the other in different anatomic locations (such as thighs or abdomen).

• Do not inject into areas where the skin is tender, bruised, erythematous, indurated or affected by any lesions. Administration of SKYRIZI in the upper, outer arm may only be performed by a healthcare professional or caregiver.

• If a dose is missed, administer the dose as soon as possible. Thereafter, resume dosing at the regular scheduled time.

The SKYRIZI “Instructions for Use” contains more detailed instructions on the preparation and administration of SKYRIZI [see Instructions for Use]. Instruct the patient to read the Instructions for Use before administration.

3 DOSAGE FORMS AND STRENGTHS

Subcutaneous Injection

SKYRIZI Pen

- Injection: 150 mg/mL as a colorless to yellow and clear to slightly opalescent solution in each single-dose prefilled pen.

SKYRIZI Prefilled Syringe

- Injection: 90 mg/mL as a colorless to slightly yellow and clear to slightly opalescent solution in each single-dose prefilled syringe.
- Injection: 150 mg/mL as a colorless to yellow and clear to slightly opalescent solution in each single-dose prefilled syringe.
- Injection: 180 mg/1.2 mL (150 mg/mL) as a colorless to yellow and clear to slightly opalescent solution in each single-dose prefilled syringe.

SKYRIZI Prefilled Cartridge with Supplied On-Body Injector

- Injection: 180 mg/1.2 mL (150 mg/mL) as a colorless to yellow, and clear to slightly opalescent solution in each single-dose prefilled cartridge for use with the on-body injector.
- Injection: 360 mg/2.4 mL (150 mg/mL) as a colorless to yellow, and clear to slightly opalescent solution in each single-dose prefilled cartridge for use with the on-body injector.

Intravenous Infusion

SKYRIZI Vial

- Injection: 600 mg/10 mL (60 mg/mL) as a colorless to slightly yellow, and clear to slightly opalescent solution in each single-dose vial.

4 CONTRAINDICATIONS

SKYRIZI is contraindicated in patients with a history of serious hypersensitivity reaction to risankizumab-rzaa or any of the excipients [see Warnings and Precautions (5.1)].

5 WARNINGS AND PRECAUTIONS

5.1 Hypersensitivity Reactions

Serious hypersensitivity reactions, including anaphylaxis, have been reported with use of SKYRIZI. If a serious hypersensitivity reaction occurs, discontinue SKYRIZI and initiate appropriate therapy immediately [see Adverse Reactions (6.1)].

5.2 Infections

SKYRIZI may increase the risk of infections [see Adverse Reactions (6.1)].

Treatment with SKYRIZI should not be initiated in patients with any clinically important active infection until the infection resolves or is adequately treated.

In patients with a chronic infection or a history of recurrent infection, consider the risks and benefits prior to prescribing SKYRIZI. Instruct patients to seek medical advice if signs or symptoms of clinically important infection occur. If a patient develops such an infection or is not responding to standard therapy, monitor the patient closely and do not administer SKYRIZI until the infection resolves.

5.3 Tuberculosis

Evaluate patients for tuberculosis (TB) infection prior to initiating treatment with SKYRIZI. Across the Phase 3 psoriasis clinical studies, of the 72 subjects with latent TB who were concurrently treated with SKYRIZI and appropriate TB prophylaxis during the studies, none developed active TB during the mean follow-up of 61 weeks on SKYRIZI. Two subjects taking isoniazid for treatment of latent TB discontinued treatment due to liver injury. Of the 31 subjects from the PsO-3 study with latent TB who did not receive prophylaxis during the study, none developed active TB during the mean follow-up of 55 weeks on SKYRIZI. Consider anti-TB therapy prior to initiating SKYRIZI in patients with a past history of latent or active TB in whom an adequate course of treatment cannot be confirmed. Monitor patients for signs and symptoms of active TB during and after SKYRIZI treatment. Do not administer SKYRIZI to patients with active TB.

5.4 Hepatotoxicity in Treatment of Inflammatory Bowel Disease

A serious adverse reaction of drug-induced liver injury in conjunction with a rash that required hospitalization was reported in a patient with Crohn’s disease (ALT 54x ULN, AST 30x ULN, and total bilirubin 2.2x ULN) following two 600 mg intravenous doses of SKYRIZI. The liver test abnormalities resolved following administration of steroids. SKYRIZI was subsequently discontinued.

For the treatment of Crohn’s disease and ulcerative colitis, evaluate liver enzymes and bilirubin at baseline, and during induction at least up to 12 weeks of treatment. Monitor thereafter according to routine patient management.

Consider other treatment options in patients with evidence of liver cirrhosis. Prompt investigation of the cause of liver enzyme elevation is recommended to identify potential cases of drug-induced liver injury. Interrupt treatment if drug-induced liver injury is suspected, until this diagnosis is excluded. Instruct patients to seek immediate medical attention if they experience symptoms suggestive of hepatic dysfunction.

5.5 Administration of Vaccines

Avoid use of live vaccines in patients treated with SKYRIZI. Medications that interact with the immune system may increase the risk of infection following administration of live vaccines. Prior to initiating therapy with SKYRIZI, complete all age-appropriate vaccinations according to current immunization guidelines. No data are available on the response to live or inactive vaccines.

6 ADVERSE REACTIONS

The following adverse reactions are discussed in other sections of labeling:

- Hypersensitivity Reactions [see Warnings and Precautions (5.1)]
- Infections [see Warnings and Precautions (5.2)]
- Tuberculosis [see Warnings and Precautions (5.3)]
- Hepatotoxicity in Treatment of Inflammatory Bowel Disease [see Warnings and Precautions (5.4)]

6.1 Clinical Trials Experience

Because clinical trials are conducted under widely varying conditions, adverse drug reaction rates observed in the clinical trials of a drug cannot be directly compared with rates in the clinical trials of another drug and may not reflect the rates observed in practice.

Plaque Psoriasis

A total of 2234 subjects were treated with SKYRIZI in clinical development trials in plaque psoriasis. Of these, 1208 subjects with psoriasis were exposed to SKYRIZI for at least one year.

Data from placebo- and active-controlled trials were pooled to evaluate the safety of SKYRIZI for up to 16 weeks. In total, 1306 subjects were evaluated in the SKYRIZI 150 mg group.

Table 2 summarizes the adverse drug reactions that occurred at a rate of at least 1% and at a higher rate in the SKYRIZI group than the placebo group during the 16-week controlled period of pooled clinical trials.

Table 2. Adverse Drug Reactions Occurring in ≥ 1% of Subjects with Plaque Psoriasis on SKYRIZI through Week 16
Adverse Drug Reactions | SKYRIZI N = 1306 n (%) | Placebo N = 300 n (%)
Upper respiratory infectionsa | 170 (13.0) | 29 (9.7)
Headacheb | 46 (3.5) | 6 (2.0)
Fatiguec | 33 (2.5) | 3 (1.0)
Injection site reactionsd | 19 (1.5) | 3 (1.0)
Tinea infectionse | 15 (1.1) | 1 (0.3)
a Includes: respiratory tract infection (viral, bacterial or unspecified), sinusitis (including acute), rhinitis, nasopharyngitis, pharyngitis (including viral), tonsillitis
b Includes: headache, tension headache, sinus headache, cervicogenic headache
c Includes: fatigue, asthenia
d Includes: injection site bruising, erythema, extravasation, hematoma, hemorrhage, infection, inflammation, irritation, pain, pruritus, reaction, swelling, warmth
e Includes: tinea pedis, tinea cruris, body tinea, tinea versicolor, tinea manuum, tinea infection, onychomycosis

Adverse drug reactions that occurred in < 1% but > 0.1% of subjects in the SKYRIZI group and at a higher rate than in the placebo group through Week 16 were folliculitis and urticaria.

Specific Adverse Drug Reactions

Infections

In the first 16 weeks, infections occurred in 22.1% of the SKYRIZI group (90.8 events per 100 subject-years) compared with 14.7% of the placebo group (56.5 events per 100 subject-years) and did not lead to discontinuation of SKYRIZI. The rates of serious infections for the SKYRIZI group and the placebo group were ≤0.4%. Serious infections in the SKYRIZI group included cellulitis, osteomyelitis, sepsis, and herpes zoster. In Studies PsO-1 and PsO-2, through Week 52, the rate of infections (73.9 events per 100 subject-years) was similar to the rate observed during the first 16 weeks of treatment.

Safety Through Week 52

Through Week 52, no new adverse reactions were identified, and the rates of the adverse reactions were similar to those observed during the first 16 weeks of treatment. During this period, serious infections that led to study discontinuation included pneumonia.

Psoriatic Arthritis

The overall safety profile observed in subjects with psoriatic arthritis treated with SKYRIZI is generally consistent with the safety profile in subjects with plaque psoriasis. Additionally, in the Phase 3 placebo-controlled trials the incidence of hepatic events was higher in the SKYRIZI group (5.4%, 16.7 events per 100 patient years) compared to the placebo group (3.9%, 12.6 events per 100 patient years). Of these, the most common events that were reported more frequently in both the placebo group and the SKYRIZI group were ALT increased (placebo: n=12 (1.7%); SKYRIZI: n=16 (2.3%)), AST increased (placebo: n=9 (1.3%); SKYRIZI: n=13 (1.8%)), and GGT increased (placebo: n=5 (0.7%); SKYRIZI: n=8 (1.1%)). There were no serious hepatic events reported. The incidence of hypersensitivity reactions was higher in the SKYRIZI group (n=16, 2.3%) compared to the placebo group (n=9, 1.3%). In the Phase 3 placebo-controlled trials, hypersensitivity reactions reported at a higher rate in the SKYRIZI group included rash (placebo: n=4 (0.6%); SKYRIZI: n=5 (0.7%), allergic rhinitis (placebo: n=1 (0.1%); SKYRIZI: n=2 (0.3%), and facial swelling (placebo: n=0 (0.0%); SKYRIZI n=1 (0.1%). One case of anaphylaxis was reported in a subject who received SKYRIZI in the Phase 2 clinical trial.

Crohn’s Disease

SKYRIZI was studied up to 12 weeks in subjects with moderately to severely active Crohn’s disease in two randomized, double-blind, placebo-controlled induction studies (CD-1, CD-2) and a randomized, double-blind, placebo-controlled, dose-finding study (CD-4; NCT02031276). Long-term safety up to 52 weeks was evaluated in subjects who responded to induction therapy in a randomized, double-blind, placebo-controlled maintenance study (CD-3) [see Clinical Studies (14.3)].

In the two induction studies (CD-1, CD-2) and the dose finding study (CD-4), 620 subjects received the SKYRIZI intravenous induction regimen at Weeks 0, 4 and 8. In the maintenance study (CD-3), 297 subjects who achieved clinical response, defined as a reduction in CDAI of at least 100 points from baseline after 12 weeks of induction treatment with intravenous SKYRIZI in studies CD-1 and CD-2, received a maintenance regimen of SKYRIZI either 180 mg or 360 mg subcutaneously at Week 12 and every 8 weeks thereafter for up to an additional 52 weeks.

Adverse reactions reported in > 3% of subjects in induction studies and at a higher rate than placebo are shown in Table 3.

Table 3. Adverse Drug Reactions Reported in > 3% of Subjects with Crohn’s Disease Treated with SKYRIZI in Placebo-Controlled 12-Week Induction Studies (CD-1, CD-2, and CD-4)
Adverse Drug Reactions | SKYRIZI 600 mg Intravenous Infusiona N = 620 n (%) | Placebo N = 432 n (%)
Upper respiratory infectionsb | 66 (10.6) | 40 (9.3)
Headachec | 41 (6.6) | 24 (5.6)
Arthralgia | 31 (5.0) | 19 (4.4)
a SKYRIZI 600 mg as an intravenous infusion at Week 0, Week 4, and Week 8.
b Includes: influenza like illness, nasopharyngitis, influenza, pharyngitis, upper respiratory tract infection, viral upper respiratory tract infection, COVID-19, nasal congestion, respiratory tract infection viral, viral pharyngitis, tonsillitis, upper respiratory tract inflammation
c Includes: headache, tension headache

Adverse reactions reported in >3% of subjects in the maintenance study and at a higher rate than placebo are shown in Table 4.

Table 4. Adverse Reactions Reported in >3% of Subjects with Crohn’s Disease Treated with SKYRIZIa in Placebo-Controlled 52-Week Maintenance Study (CD-3)
Adverse Drug Reactions | SKYRIZI 180 mg Subcutaneous Injection N = 155 n (%) | SKYRIZI 360 mg Subcutaneous Injection N = 142 n (%) | Placebo N = 143 n (%)
Arthralgia | 13 (8.4) | 13 (9.2) | 12 (8.4)
Abdominal painb | 9 (5.8) | 12 (8.5) | 6 (4.2)
Injection site reactionsc,d | 7 (4.5) | 8 (5.6) | 4 (2.8)
Anemia | 7 (4.5) | 7 (4.9) | 6 (4.2)
Pyrexia | 4 (2.6) | 7 (4.9) | 4 (2.8)
Back pain | 3 (1.9) | 6 (4.2) | 3 (2.1)
Arthropathy | 1 (0.6) | 5 (3.5) | 2 (1.4)
Urinary tract infection | 1 (0.6) | 5 (3.5) | 4 (2.8)
a SKYRIZI 180 mg or 360 mg at Week 12 and every 8 weeks thereafter for up to an additional 52 weeks
b Includes: abdominal pain, abdominal pain upper, abdominal pain lower
c Includes: injection site rash, injection site erythema, injection site swelling, injection site urticaria, injection site warmth, injection site pain, injection site hypersensitivity, injection site reaction
d Some subjects had multiple occurrences of injection site reactions. In this table, injection site reactions are counted only once per subject for the rate calculations.

Specific Adverse Drug Reactions

Infections

In the maintenance study (CD-3) through Week 52, the rate of infections was 32.3% (50.2 events per 100 subject-years) in subjects who received SKYRIZI 180 mg and 36.6% (60.8 events per 100 subject-years) in subjects who received SKYRIZI 360 mg compared to 36.4% (60.3 events per 100 subject-years) in subjects who received placebo after SKYRIZI induction. The rate of serious infections was 2.6% (2.7 events per 100 subject-years) in subjects who received SKYRIZI 180 mg and 5.6% (7.4 events per 100 subject-years) in subjects who received SKYRIZI 360 mg compared to 2.1% (2.4 events per 100 subject-years) in subjects who received placebo after SKYRIZI induction.

Lipid Elevations

Elevations in lipid parameters (total cholesterol and low-density lipoprotein cholesterol [LDL-C]) were first assessed at 4 weeks following initiation of SKYRIZI in the induction trials (CD-1, CD-2). Increases from baseline and increases relative to placebo were observed at Week 4 and remained stable to Week 12. Following SKYRIZI induction, mean total cholesterol increased by 9.4 mg/dL from baseline to a mean absolute value of 175.1 mg/dL at Week 12. Similarly, mean LDL-C increased by 6.6 mg/dL from baseline to a mean absolute value of 92.6 mg/dL at Week 12. Mean LDL-C increased by 3.1 mg/dL from baseline to a mean absolute value of 99.0 mg/dL at Week 52 with SKYRIZI 180 mg maintenance treatment and by 2.3 mg/dL from baseline to a mean absolute value of 102.2 mg/dL at Week 52 with SKYRIZI 360 mg maintenance treatment (CD-3).

Ulcerative Colitis

SKYRIZI was studied up to 12 weeks in subjects with moderately to severely active ulcerative colitis in a randomized, double-blind, placebo-controlled induction study (UC-1) and a randomized, double-blind, placebo-controlled, dose-finding study (UC-3). Long-term safety up to 52 weeks was evaluated in subjects who responded to induction therapy in a randomized, double-blind, placebo-controlled maintenance study (UC-2) [see Clinical Studies (14.4)].

In the induction studies (UC-1 and UC-3), 712 subjects received the SKYRIZI 1,200 mg intravenous induction regimen at Weeks 0, 4 and 8. In the maintenance study (UC-2), 347 subjects who achieved clinical response, defined as a decrease in mMS of ≥2 points and ≥30% from baseline and a decrease in RBS ≥1 from baseline or an absolute RBS ≤1, received a maintenance regimen of SKYRIZI either 180 mg or 360 mg subcutaneously at Week 12 and every 8 weeks thereafter for up to an additional 52 weeks.

The adverse reaction reported in ≥3% subjects treated with SKYRIZI in the ulcerative colitis induction studies (UC-1 and UC-3) and at a higher rate than placebo was arthralgia (3% SKYRIZI vs 1% placebo).

Adverse reactions reported in ≥3% of subjects treated with SKYRIZI in the maintenance study (UC-2) and at a higher rate than placebo are shown in Table 5.

Table 5. Adverse Reactions Reported in ≥3% of Subjects with Ulcerative Colitis Treated with SKYRIZIa in Placebo-Controlled 52-Week Maintenance Study (UC-2)
Adverse Drug Reactions | SKYRIZI 180 mg Subcutaneous Injection N = 170 n (%) | SKYRIZI 360 mg Subcutaneous Injection N = 177 n (%) | Placebo N = 173 n (%)
Arthralgia | 9 (5.3) | 17 (9.6) | 8 (4.6)
Pyrexia | 8 (4.7) | 7 (4.0) | 6 (3.5)
Injection site reactionsb,c | 5 (2.9) | 5 (2.8) | 2 (1.2)
Rashd | 7 (4.1) | 1 (0.6) | 3 (1.7)
a SKYRIZI 180 mg or 360 mg at Week 12 and every 8 weeks thereafter for up to an additional 52 weeks
b Includes: application site pain, injection site erythema, injection site pain, injection site pruritus, injection site reaction
c Some subjects had multiple occurrences of injection site reactions. In this table, injection site reactions are counted only once per subject for the rate calculations.
d Includes: rash and rash macular

Specific Adverse Drug Reactions

The rates of infections, serious infections, and lipid elevations in subjects with UC who received SKYRIZI compared to subjects who received placebo in the induction studies (UC-1 and UC-3) and maintenance study (UC-2) were similar to the rates in subjects with CD who received SKYRIZI compared to subjects who received placebo in the induction studies (CD-1, CD-2, and CD-4) and maintenance study (CD-3).

6.2 Immunogenicity

As with all therapeutic proteins, there is potential for immunogenicity. The detection of antibody formation is highly dependent on the sensitivity and specificity of the assay. Additionally, the observed incidence of antibody (including neutralizing antibody) positivity in an assay may be influenced by several factors including assay methodology, sample handling, timing of sample collection, concomitant medications, and underlying disease. For these reasons, comparison of the incidence of antibodies in the studies described below with the incidence of antibodies in other studies or to other products, including other risankizumab products, may be misleading.

Plaque Psoriasis

By Week 52, approximately 24% (263/1079) of subjects treated with SKYRIZI at the recommended dose developed antibodies to risankizumab-rzaa. Of the subjects who developed antibodies to risankizumab-rzaa, approximately 57% (14% of all subjects treated with SKYRIZI) had antibodies that were classified as neutralizing. Higher antibody titers in approximately 1% of subjects treated with SKYRIZI were associated with lower risankizumab-rzaa concentrations and reduced clinical response.

Psoriatic Arthritis

By Week 28, approximately 12.1% (79/652) of subjects treated with SKYRIZI at the recommended dose developed antibodies to risankizumab-rzaa. None of the subjects who developed antibodies to risankizumab-rzaa had antibodies that were classified as neutralizing. Antibodies to risankizumab-rzaa were not associated with changes in clinical response for psoriatic arthritis. A higher proportion of subjects with anti-drug antibodies experienced hypersensitivity reactions (6.3% (5/79)) and injection site reactions (2.5% (2/79)) compared to subjects without anti-drug antibodies (3.8% (22/574) with hypersensitivity reactions and 0.7% (4/574) with injection site reactions). None of these hypersensitivity and injection site reactions led to discontinuation of risankizumab-rzaa.

Crohn’s Disease

By Week 64, antibodies to risankizumab-rzaa developed in approximately 3.4% (2/58) of subjects treated with SKYRIZI induction followed by 360 mg maintenance regimen. No subjects (0/57) treated with SKYRIZI induction followed by 180 mg maintenance regimen developed antibodies to risankizumab-rzaa. None of the subjects who developed antibodies to risankizumab-rzaa had antibodies that were classified as neutralizing.

Ulcerative Colitis

By Week 64, antibodies to risankizumab-rzaa developed in approximately 8.9% (8/90) or 4.4% (4/91) of subjects treated with SKYRIZI induction followed by the 180 mg or 360 mg maintenance regimen, respectively. Of the subjects who developed antibodies to risankizumab-rzaa, 75% (6.7% of all subjects treated with SKYRIZI induction followed by the 180 mg maintenance regimen) or 50% (2.2% of all subjects treated with SKYRIZI induction followed by the 360 mg maintenance regimen), respectively, had antibodies that were classified as neutralizing.

6.3 Postmarketing Experience

The following adverse reactions have been reported during post-approval of SKYRIZI. Because these reactions are reported voluntarily from a population of uncertain size, it is not always possible to reliably estimate their frequency or establish a causal relationship to SKYRIZI exposure:

- Skin and subcutaneous tissue disorders: eczema and rash

8 USE IN SPECIFIC POPULATIONS

8.1 Pregnancy

Pregnancy Exposure Registry

There is a pregnancy exposure registry that monitors outcomes in women who become pregnant while treated with SKYRIZI. Patients should be encouraged to enroll by calling 1-877-302-2161 or visiting http://glowpregnancyregistry.com.

Risk Summary

Available pharmacovigilance and clinical trial data with risankizumab use in pregnant women are insufficient to establish a drug-associated risk of major birth defects, miscarriage or other adverse maternal or fetal outcomes. Although there are no data on risankizumab-rzaa, monoclonal antibodies can be actively transported across the placenta, and SKYRIZI may cause immunosuppression in the in utero-exposed infant. There are adverse pregnancy outcomes in women with inflammatory bowel disease (see Clinical Considerations).

In an enhanced pre- and post-natal developmental toxicity study, pregnant cynomolgus monkeys were administered subcutaneous doses of 5 or 50 mg/kg risankizumab-rzaa once weekly during the period of organogenesis up to parturition. Increased fetal/infant loss was noted in pregnant monkeys at the 50 mg/kg dose (see Data). The 50 mg/kg dose in pregnant monkeys resulted in approximately 5 times the exposure (AUC) in humans administered the maximum recommended induction dose (1,200 mg) and 32 times the exposure (AUC) to the maximum recommended maintenance dose (360 mg). No risankizumab-rzaa-related effects on functional or immunological development were observed in infant monkeys from birth through 6 months of age. The clinical significance of these findings for humans is unknown.

All pregnancies have a background risk of birth defect, loss, or other adverse outcomes. The background risk of major birth defects and miscarriage for the indicated population is unknown. In the U.S. general population, the estimated background risk of major birth defects and miscarriage in clinically recognized pregnancies is 2% to 4% and 15% to 20%, respectively.

Clinical Considerations

Disease-associated maternal and embryo/fetal risk

Published data suggest that the risk of adverse pregnancy outcomes in women with inflammatory bowel disease is associated with increased disease activity. Adverse pregnancy outcomes include preterm delivery (before 37 weeks of gestation), low birth weight (less than 2,500 g) infants, and small for gestational age at birth.

Fetal/Neonatal adverse reactions

Transport of endogenous IgG antibodies across the placenta increases as pregnancy progresses, and peaks during the third trimester. Because risankizumab may interfere with immune response to infections, risks and benefits should be considered prior to administering live vaccines to infants exposed to SKYRIZI in utero. There are insufficient data regarding infant serum levels of risankizumab at birth and the duration of persistence of risankizumab in infant serum after birth. Although a specific timeframe to delay live virus immunizations in infants exposed in utero is unknown, a minimum of 5 months after birth should be considered because of the half-life of the product.

Data

Animal Data

An enhanced pre- and post-natal developmental toxicity study was conducted in cynomolgus monkeys. Pregnant cynomolgus monkeys were administered weekly subcutaneous doses of risankizumab-rzaa of 5 or 50 mg/kg from gestation day 20 to parturition, and the cynomolgus monkeys (mother and infants) were monitored for 6 months after delivery. No maternal toxicity was noted in this study. There were no treatment-related effects on growth and development, malformations, developmental immunotoxicology, or neurobehavioral development. However, a dose-dependent increase in fetal/infant loss was noted in the risankizumab-rzaa-treated groups (32% and 43% in the 5 mg/kg and 50 mg/kg groups, respectively) compared with the vehicle control group (19%). The increased fetal/infant loss in the 50 mg/kg group was considered to be related to risankizumab-rzaa treatment. The no-observed adverse effect level (NOAEL) for maternal toxicity was identified as 50 mg/kg, and the NOAEL for developmental toxicity was identified as 5 mg/kg. The 5 mg/kg dose in pregnant monkeys resulted in approximately 0.6 times the exposure (AUC) in humans administered the maximum recommended induction dose (1,200 mg) and 5 times the exposure (AUC) in humans administered the maximum recommended maintenance dose (360 mg). In the infants, mean serum concentrations increased in a dose-dependent manner and were approximately 17%-86% of the respective maternal concentrations. Following delivery, most adult female cynomolgus monkeys and all infants from the risankizumab-rzaa-treated groups had measurable serum concentrations of risankizumab-rzaa up to 91 days postpartum. Serum concentrations were below detectable levels at 180 days postpartum.

8.2 Lactation

Risk Summary

There are no data on the presence of risankizumab-rzaa in human milk, the effects on the breastfed infant, or the effects on milk production. Endogenous maternal IgG and monoclonal antibodies are transferred in human milk. The effects of local gastrointestinal exposure and limited systemic exposure in the breastfed infant to risankizumab-rzaa are unknown. The developmental and health benefits of breastfeeding should be considered along with the mother's clinical need for SKYRIZI and any potential adverse effects on the breastfed infant from SKYRIZI or from the underlying maternal condition.

8.4 Pediatric Use

The safety and effectiveness of SKYRIZI have not been established in pediatric patients.

8.5 Geriatric Use

Of the 6,862 subjects exposed to SKYRIZI, a total of 664 were 65 years or older (243 subjects with plaque psoriasis, 246 subjects with psoriatic arthritis, 72 subjects with Crohn’s disease and 103 subjects with ulcerative colitis), and 71 subjects were 75 years or older.

Clinical studies of SKYRIZI, within each indication, did not include sufficient numbers of subjects 65 years of age and older to determine whether they respond differently from younger adult subjects.

No clinically meaningful differences in the pharmacokinetics of risankizumab-rzaa were observed based on age[see Clinical Pharmacology (12.3)].

11 DESCRIPTION

Risankizumab-rzaa, an interleukin-23 (IL-23) antagonist, is a humanized immunoglobulin G1 (IgG1) monoclonal antibody. Risankizumab-rzaa is produced by recombinant DNA technology in Chinese hamster ovary cells and has an approximate molecular weight of 149 kDa.

SKYRIZI (risankizumab-rzaa) injection 90 mg/mL prefilled syringe for subcutaneous use

Each SKYRIZI prefilled syringe contains a sterile, preservative-free, colorless to slightly yellow, and clear to slightly opalescent solution. Each syringe delivers 90 mg of risankizumab-rzaa, and inactive ingredients polysorbate 20 (0.2 mg), sodium succinate (0.63 mg), sorbitol (41 mg), succinic acid (0.059 mg), and Water for Injection, USP. The pH is 6.2.

SKYRIZI (risankizumab-rzaa) injection 150 mg/mL prefilled syringe or prefilled pen for subcutaneous use

Each SKYRIZI prefilled pen or prefilled syringe contains a sterile, preservative-free, colorless to yellow, and clear to slightly opalescent solution. Each syringe and pen delivers 150 mg of risankizumab-rzaa and the inactive ingredients glacial acetic acid (0.054 mg), polysorbate 20 (0.2 mg), sodium acetate (0.75 mg), trehalose (63.33 mg), and Water for Injection, USP. The pH is 5.7.

SKYRIZI (risankizumab-rzaa) injection 180 mg/1.2 mL prefilled syringe for subcutaneous use

Each SKYRIZI prefilled syringe contains a sterile, preservative-free, colorless to yellow, and clear to slightly opalescent solution. Each syringe delivers 180 mg of risankizumab-rzaa, and inactive ingredients glacial acetic acid (0.065 mg), polysorbate 20 (0.24 mg), sodium acetate (0.898 mg), trehalose (76.0 mg), and Water for Injection, USP. The pH is 5.7.

SKYRIZI (risankizumab-rzaa) injection 180 mg/1.2 mL (150 mg/mL) prefilled cartridge for use with supplied on-body-injector for subcutaneous use

Each SKYRIZI prefilled cartridge contains a sterile, preservative-free, colorless to yellow, and clear to slightly opalescent solution. Each cartridge delivers 180 mg of risankizumab-rzaa, and the inactive ingredients glacial acetic acid (0.065 mg), polysorbate 20 (0.24 mg), sodium acetate (0.9 mg), trehalose (76 mg), and Water for Injection, USP. The pH is 5.7.

SKYRIZI (risankizumab-rzaa) injection 360 mg/2.4 mL (150 mg/mL) prefilled cartridge for use with the supplied on-body injector for subcutaneous use

Each SKYRIZI prefilled cartridge contains a sterile, preservative-free, colorless to yellow, and clear to slightly opalescent solution. Each cartridge delivers 360 mg of risankizumab-rzaa, and the inactive ingredients glacial acetic acid (0.13 mg), polysorbate 20 (0.48 mg), sodium acetate (1.8 mg), trehalose (152 mg), and Water for Injection, USP. The pH is 5.7.

SKYRIZI 600 mg/10 mL (60 mg/mL) in a vial for intravenous infusion

SKYRIZI (risankizumab-rzaa) injection 600 mg/10 mL (60 mg/mL) is a sterile, preservative-free, colorless to slightly yellow, and clear to slightly opalescent solution in a 10 mL single-dose vial.

Each 10 mL single-dose vial contains 600 mg of risankizumab-rzaa, and the inactive ingredients glacial acetic acid (0.54 mg), polysorbate 20 (2 mg), sodium acetate (7.5 mg), trehalose (633.3 mg), and Water for Injection, USP. The pH is 5.7.

12 CLINICAL PHARMACOLOGY

12.1 Mechanism of Action

Risankizumab-rzaa is a humanized IgG1 monoclonal antibody that selectively binds to the p19 subunit of human IL-23 cytokine and inhibits its interaction with the IL-23 receptor. IL-23 is a naturally occurring cytokine that is involved in inflammatory and immune responses.

Risankizumab-rzaa inhibits the release of pro-inflammatory cytokines and chemokines.

12.2 Pharmacodynamics

No formal pharmacodynamics studies have been conducted with risankizumab-rzaa.

12.3 Pharmacokinetics

Risankizumab-rzaa plasma concentrations, after single dose administration increased dose proportionally from 18 mg to 360 mg when administered subcutaneously (0.12 to 2.4 times the lowest recommended dose and 0.05 to 1 times the highest recommended dose) and from 200 mg to 1,800 mg when administered as an up to 3-hour intravenous infusion (0.2 to 3 times the recommended dose) in healthy subjects.

In subjects with plaque psoriasis treated with 150 mg subcutaneously at Weeks 0, 4, and every 12 weeks thereafter, steady-state peak concentration (Cmax) and trough concentration (Ctrough) are estimated to be 12 mcg/mL and 2 mcg/mL, respectively.

With the same subcutaneous dosing regimen, the pharmacokinetics of risankizumab-rzaa in subjects with psoriatic arthritis were similar to that in subjects with plaque psoriasis.

In subjects with Crohn’s disease treated with 600 mg intravenous induction dose at Weeks 0, 4, and 8, followed by 180 mg or 360 mg subcutaneous maintenance dose at Week 12 and every 8 weeks thereafter, the median Cmax and Ctrough are estimated to be 156 mcg/mL and 38.8 mcg/mL, respectively, during Weeks 8-12; and the steady state median Cmax and Ctrough are estimated to be 14.0 mcg/mL and 4.1 mcg/mL, respectively for 180 mg or 28.0 mcg/mL and 8.1 mcg/mL, respectively, for 360 mg, during Weeks 40-48.

In subjects with ulcerative colitis treated with 1,200 mg intravenous induction dose at Weeks 0, 4, and 8, followed by 180 mg or 360 mg subcutaneous maintenance dose at Week 12 and every 8 weeks thereafter, the median Cmax and Ctrough are estimated to be 350 and 87.7 mcg/mL, respectively, during the induction period (Weeks 8-12); and the steady state median Cmax and Ctrough are estimated to be 19.6 and 4.64 µg/mL, respectively, for 180 mg or 39.2 mcg/mL and 9.29 mcg/mL, respectively, for 360 mg, during the maintenance period (Weeks 40-48).

Based on population pharmacokinetic analyses, the pharmacokinetics of risankizumab-rzaa in subjects with ulcerative colitis was generally similar to that in subjects with Crohn’s disease.

Absorption

The absolute bioavailability of risankizumab-rzaa was estimated to be 74 to 89% following subcutaneous injection. In healthy subjects, following administration of a single subcutaneous dose, Cmax was reached by 3 to 14 days.

Distribution

The estimated steady-state volume of distribution (inter-subject CV%) was 11.2 L (34%) in subjects with plaque psoriasis, and 7.68 L (64%) in subjects with Crohn’s disease.

Elimination

The estimated systemic clearance (inter-subject CV%) was 0.31 L/day (24%) and 0.30 L/day (34%) and terminal elimination half-life was approximately 28 days and 21 days in subjects with plaque psoriasis and Crohn’s disease, respectively.

Metabolism

The metabolic pathway of risankizumab-rzaa has not been characterized. As a humanized IgG1 monoclonal antibody, risankizumab-rzaa is expected to be degraded into small peptides and amino acids via catabolic pathways in a manner similar to endogenous IgG.

Specific Populations

Risankizumab-rzaa exposures (Ctrough) in geriatric patients (≥65 years) are comparable to those in younger adult patients within each indication. No studies have been conducted to determine the effect of renal or hepatic impairment on the pharmacokinetics of risankizumab-rzaa.

Body Weight

Risankizumab-rzaa clearance and volume of distribution increase and plasma concentrations decrease as body weight increases; however, no dose adjustment is recommended based on body weight.

Drug Interaction Studies

Cytochrome P450 Substrates

No clinically significant changes in exposure of caffeine (CYP1A2 substrate), warfarin (CYP2C9 substrate), omeprazole (CYP2C19 substrate), metoprolol (CYP2D6 substrate), or midazolam (CYP3A substrate) were observed when used concomitantly with risankizumab-rzaa in subjects with plaque psoriasis (risankizumab-rzaa 150 mg administered subcutaneously at Weeks 0, 4, 8, and 12) and subjects with Crohn’s disease or ulcerative colitis (risankizumab-rzaa 1,800 mg administered intravenously at Weeks 0, 4, and 8, i.e., 3 times and 1.5 times the recommended dose for Crohn’s disease and ulcerative colitis, respectively).

13 NONCLINICAL TOXICOLOGY

13.1 Carcinogenesis, Mutagenesis, Impairment of Fertility

Carcinogenicity and mutagenicity studies have not been conducted with SKYRIZI.

No effects on male fertility parameters were observed in sexually mature male cynomolgus monkeys dosed weekly for 26 weeks with 50 mg/kg risankizumab-rzaa at 4 times the exposure (AUC) in humans administered the maximum recommended induction dose (1,200 mg) and 39 times the exposure in humans administered the maximum recommended maintenance dose (360 mg).

14 CLINICAL STUDIES

14.1 Plaque Psoriasis

Four multicenter, randomized, double-blind studies [PsO-1 (NCT02684370), PsO-2 (NCT02684357), PsO-3 (NCT02672852), and PsO-4 (NCT02694523)] enrolled 2,109 subjects 18 years of age and older with moderate to severe plaque psoriasis who had a body surface area (BSA) involvement of ≥10%, a static Physician’s Global Assessment (sPGA) score of ≥3 (“moderate”) in the overall assessment (plaque thickness/induration, erythema, and scaling) of psoriasis on a severity scale of 0 to 4, and a Psoriasis Area and Severity Index (PASI) score ≥12.

Overall, subjects had a median baseline PASI score of 17.8 and a median BSA of 20%. Baseline sPGA score was 4 (“severe”) in 19% of subjects. A total of 10% of study subjects had a history of diagnosed psoriatic arthritis.

Across all studies, 38% of subjects had received prior phototherapy, 48% had received prior non-biologic systemic therapy, and 42% had received prior biologic therapy for the treatment of psoriasis.

Studies PsO-1 and PsO-2

In studies PsO-1 and PsO-2, 997 subjects were enrolled (including 598 subjects randomized to the SKYRIZI 150 mg group, 200 subjects randomized to the placebo group, and 199 to the biologic active control group). Subjects received treatment at Weeks 0, 4, and every 12 weeks thereafter.

Both studies assessed the responses at Week 16 compared with placebo for the two co-primary endpoints:

- the proportion of subjects who achieved an sPGA score of 0 (“clear”) or 1 (“almost clear”)
- the proportion of subjects who achieved at least a 90% reduction from baseline PASI (PASI 90)

Secondary endpoints included the proportion of subjects who achieved PASI 100, sPGA 0, and Psoriasis Symptom Scale (PSS) 0 at Week 16.

The results are presented in Table 6.

Table 6. Efficacy Results at Week 16 in Adults with Plaque Psoriasis in PsO-1 and PsO-2
 | PsO-1 |  | PsO-2
 | SKYRIZI (N=304) n (%) | Placebo (N=102) n (%) | SKYRIZI (N=294) n (%) | Placebo (N=98) n (%)
sPGA 0 or 1 (“clear or almost clear”) a | 267 (88) | 8 (8) | 246 (84) | 5 (5)
PASI 90 a | 229 (75) | 5 (5) | 220 (75) | 2 (2)
sPGA 0 (“clear”) | 112 (37) | 2 (2) | 150 (51) | 3 (3)
PASI 100 | 109 (36) | 0 (0) | 149 (51) | 2 (2)
a Co-primary endpoints

Examination of age, gender, race, body weight, baseline PASI score and previous treatment with systemic or biologic agents did not identify differences in response to SKYRIZI among these subgroups at Week 16.

In PsO-1 and PsO-2 at Week 52, subjects receiving SKYRIZI achieved sPGA 0 (58% and 60%, respectively), PASI 90 (82% and 81%, respectively), and PASI 100 (56% and 60%, respectively).

Patient Reported Outcomes

Improvements in signs and symptoms related to pain, redness, itching and burning at Week 16 compared to placebo were observed in both studies as assessed by the PSS. In PsO-1 and PsO-2, about 30% of the subjects who received SKYRIZI achieved PSS 0 (“none”) at Week 16 compared to 1% of the subjects who received placebo.

Study PsO-3

Study PsO-3 enrolled 507 subjects (407 randomized to SKYRIZI 150 mg and 100 to placebo). Subjects received treatment at Weeks 0, 4, and every 12 weeks thereafter.

At Week 16, SKYRIZI was superior to placebo on the co-primary endpoints of sPGA 0 or 1 (84% SKYRIZI and 7% placebo) and PASI 90 (73% SKYRIZI and 2% placebo). The respective response rates for SKYRIZI and placebo at Week 16 were: sPGA 0 (46% SKYRIZI and 1% placebo); PASI 100 (47% SKYRIZI and 1% placebo); and PASI 75 (89% SKYRIZI and 8% placebo).

Maintenance and Durability of Response

In PsO-1 and PsO-2, among the subjects who received SKYRIZI and had PASI 100 at Week 16, 80% (206/258) of the subjects who continued on SKYRIZI had PASI 100 at Week 52. For PASI 90 responders at Week 16, 88% (398/450) of the subjects had PASI 90 at Week 52.

In PsO-3, subjects who were originally on SKYRIZI and had sPGA 0 or 1 at Week 28 were re-randomized to continue SKYRIZI every 12 weeks or withdrawal of therapy. At Week 52, 87% (97/111) of the subjects re-randomized to continue treatment with SKYRIZI had sPGA 0 or 1 compared to 61% (138/225) who were re-randomized to withdrawal of SKYRIZI.

14.2 Psoriatic Arthritis

The safety and efficacy of SKYRIZI were assessed in 1407 subjects in 2 randomized, double-blind, placebo-controlled studies (964 in PsA-1 [NCT03675308] and 443 in PsA-2 [NCT03671148]) in subjects 18 years and older with active psoriatic arthritis (PsA).

Subjects in these studies had a diagnosis of PsA for at least 6 months based on the Classification Criteria for Psoriatic Arthritis (CASPAR), a median duration of PsA of 4.9 years at baseline, ≥ 5 tender joints and ≥ 5 swollen joints, and active plaque psoriasis or psoriatic nail disease at baseline. Regarding baseline clinical presentation, 55.9% of subjects had ≥3% BSA with active plaque psoriasis; 63.4% and 27.9% of subjects had enthesitis and dactylitis, respectively. In PsA-1 where psoriatic nail disease was further assessed, 67.3% had psoriatic nail disease.

In PsA-1, all subjects had a previous inadequate response or intolerance to non-biologic DMARD therapy and were biologic naïve. In PsA-2, 53.5% of subjects had a previous inadequate response or intolerance to non-biologic DMARD therapy, and 46.5% of subjects had a previous inadequate response or intolerance to biologic therapy.

In both studies, subjects were randomized to receive SKYRIZI 150 mg or placebo at Weeks 0, 4, and 16. Starting from Week 28, all subjects received SKYRIZI every 12 weeks. Both studies included a long-term extension for up to an additional 204 weeks. Regarding use of concomitant medications, 59.6% of subjects were receiving concomitant methotrexate (MTX), 11.6% were receiving concomitant non-biologic DMARDs other than MTX, and 28.9% were receiving SKYRIZI monotherapy.

For both studies, the primary endpoint was the proportion of subjects who achieved an American College of Rheumatology (ACR) 20 response at Week 24.

Clinical Response

In both studies, treatment with SKYRIZI resulted in significant improvement in measures of disease activity compared with placebo at Week 24. See Tables 7 and 8 for key efficacy results.

In both studies, similar responses were seen regardless of concomitant non-biologic DMARD use, number of prior non-biologic DMARDs, age, gender, race, and BMI. In PsA-2, responses were seen regardless of prior biologic therapy.

Table 7. Efficacy Results in Study PsA-1
Endpoint | Placebo N=481 Response Rate | SKYRIZI N=483 Response Rate | Difference from Placebo (95% CI)
ACR20 Response*
Week 16 | 33.4% | 56.3%a | 23.1% (16.8, 29.4)
Week 24 | 33.5% | 57.3%a | 24.0% (18.0, 30.0)
ACR50 Response*
Week 16 | 11.1% | 26.4% | 15.4% (10.6, 20.2)
Week 24 | 11.3% | 33.4 % | 22.2% (17.3, 27.2)
ACR70 Response*
Week 16 | 2.7% | 11.8% | 9.2% (6.1, 12.4)
Week 24 | 4.7% | 15.3% | 10.5% (6.9, 14.2)
a. multiplicity-controlled p≤0.001, SKYRIZI vs. placebo comparison.
*A Subject was considered as a non-responder after initiation of rescue medication or concomitant medications for PsA that could meaningfully impact efficacy assessment.

Table 8. Efficacy Results in Study PsA-2
Endpoint | Placebo N=219 Response Rate | SKYRIZI N=224 Response Rate | Difference from Placebo (95% CI)
ACR20 Response*
Week 16 | 25.3% | 48.3% a | 22.6% (13.9, 31.2)
Week 24 | 26.5% | 51.3% a | 24.5% (15.9, 33.0)
ACR50 Response*
Week 16 | 6.8% | 20.3% | 13.5% (7.3, 19.7)
Week 24 | 9.3% | 26.3% | 16.6% (9.7, 23.6)
ACR70 Response*
Week 16 | 3.4% | 11.2% | 7.8% (3.0, 12.6)
Week 24 | 5.9% | 12.0% | 6.0% (0.8, 11.3)
a. multiplicity-controlled p≤0.001, SKYRIZI vs. placebo comparison.
*A Subject was considered as a non-responder after initiation of rescue medication or concomitant medications for PsA that could meaningfully impact efficacy assessment.

The percent of subjects achieving ACR20 responses in study PsA-1 through Week 24 is shown in Figure 1.

Figure 1. Percent of Subjects Achieving ACR20 Responses in Study PsA-1 through Week 24

The results of the components of the ACR response criteria for both studies are shown in Table 9.

Table 9. Mean Change from Baseline in ACR Components
 | PsA-1 |  | PsA-2
 | Placebo (N=481) Mean (SD) | SKYRIZI (N=483) Mean (SD) | Placebo (N=219) Mean (SD) | SKYRIZI (N=224) Mean (SD)
Number of Swollen Joints (0-66)
Baseline | 12.2 (8.0) | 12.1 (7.8) | 13.6 (9.0) | 13.0 (8.7)
Mean change at Week 16 | -5.5 (7.0) | -7.7 (7.2) | -5.4 (8.5) | -8.0 (7.4)
Mean change at Week 24 | -6.7 (7.2) | -8.7 (7.2) | -6.5 (7.8) | -9.1 (7.6)
Number of Tender Joints (0-68)
Baseline | 20.5 (12.8) | 20.8 (14.0) | 22.3 (13.8) | 22.8 (14.9)
Mean change at Week 16 | -6.3 (11.1) | -10.7 (11.4) | -6.0 (13.1) | -11.3 (13.0)
Mean change at Week 24 | -7.9 (10.7) | -12.0 (12.3) | -8.3 (11.3) | -13.0 (12.5)
Patient’s Assessment of Pain a
Baseline | 57.1 (22.6) | 57.1 (22.6) | 57.0 (23.1) | 55.0 (23.5)
Mean change at Week 16 | -8.6 (23.7) | -18.4 (26.3) | -5.7 (22.7) | -14.4 (26.4)
Mean change at Week 24 | -10.9 (25.4) | -21.4 (26.5) | -8.7 (25.3) | -15.3 (26.5)
Patient’s Global Assessment a
Baseline | 57.4 (22.1) | 57.9 (21.7) | 56.2 (23.0) | 56.2 (21.8)
Mean change at Week 16 | -10.2 (23.9) | -19.4 (25.7) | -4.9 (23.6) | -17.0 (27.1)
Mean change at Week 24 | -11.1 (25.1) | -22.6 (26.9) | -8.7 (25.4) | -17.7 (27.7)
Physician Global Assessment a
Baseline | 62.4 (17.0) | 61.3 (17.6) | 60.7 (16.4) | 63.0 (17.0)
Mean change at Week 16 | -18.3 (22.5) | -31.1 (23.4) | -19.0 (23.3) | -32.7 (24.7)
Mean change at Week 24 | -22.2 (22.8) | -34.8 (23.2) | -21.3 (25.2) | -35.5 (25.6)
Health Assessment Questionnaire - Disability Index (HAQ-DI) b
Baseline | 1.2 (0.7) | 1.2 (0.7) | 1.1 (0.6) | 1.1 (0.6)
Mean change at Week 16 | -0.1 (0.5) | -0.3 (0.5) | -0.1 (0.5) | -0.2 (0.5)
Mean change at Week 24 | -0.1 (0.5) | -0.3 (0.5) | -0.1 (0.4) | -0.2 (0.5)
High sensitivity C-reactive protein (hs-CRP) mg/L
Baseline | 11.3 (14.1) | 11.9 (15.9) | 8.2 (17.1) | 7.4 (10.9)
Mean change at Week 16 | -0.3 (14.7) | -4.8 (14.2) | -0.1 (6.8) | -2.1 (7.5)
Mean change at Week 24 | -0.2 (11.7) | -4.3 (12.8) | -0.5 (14.5) | -1.8 (13.4)
SD= Standard Deviation.
a. Assessment based on Visual Analog Scale (100 mm) with the left end indicating “no pain” (for patient’s assessment of pain), “very well” (for patient global assessment), or “no arthritis activity” (for physician global assessment) and the right end indicating “the worst possible pain” (for patient assessment of pain), “poor” (for patient global assessment), or “extremely active arthritis” (for physician global assessment).
b. Disability Index of the Health Assessment Questionnaire; 0 = no difficulty to 3 = inability to perform, measures the patient’s ability to perform the following: dressing, arising, eating, walking, hygiene, reaching, gripping, and activities of daily living.

Treatment with SKYRIZI resulted in improvement in dactylitis and enthesitis in subjects with pre-existing dactylitis or enthesitis.

In patients with coexistent plaque psoriasis receiving SKYRIZI, the skin lesions of psoriasis improved with treatment, relative to placebo, as measured by the Psoriasis Area Severity Index (PASI 90) at Week 24.

Physical Function

In both studies, patients treated with SKYRIZI showed statistically significant improvement from baseline in physical function compared with placebo as assessed by HAQ-DI at Week 24 (Table 7). The mean difference (95% CI) from placebo in HAQ-DI change from baseline at Week 24 was -0.20 (-0.26, -0.14) in study PsA-1 and -0.16 (-0.26, -0.07) in study PsA-2.

In both studies, a greater proportion of subjects achieved a reduction of at least 0.35 in HAQ-DI score from baseline in the SKYRIZI group compared with placebo at Week 24.

Other Health Related Outcomes

In both studies, general health status was assessed by the 36-Item Short Form Health Survey (SF-36 V2). Fatigue was assessed by Functional Assessment of Chronic Illness Therapy Fatigue Scale (FACIT-Fatigue).

In both studies at Week 24, subjects treated with SKYRIZI showed improvements in the SF-36 physical component summary scores compared with subjects who received placebo. There were also numerical improvements in subjects treated with SKYRIZI in physical functioning, role physical, bodily pain, general health, vitality, social functioning, mental health, role emotional domain scores and mental component summary scores in both studies at week 24 compared to placebo. In both studies at Week 24, subjects treated with SKYRIZI showed improvements in FACIT-Fatigue scores compared with subjects who received placebo.

14.3 Crohn’s Disease

Induction Trials (Studies CD-1 and CD-2)

In two 12-week induction studies (CD-1; NCT03105128 and CD-2; NCT03104413), subjects with moderately to severely active Crohn’s disease were randomized to receive SKYRIZI 600 mg, SKYRIZI 1,200 mg, or placebo as an intravenous infusion at Week 0, Week 4, and Week 8. Moderately to severely active CD was defined as a Crohn’s Disease Activity Index (CDAI) of 220 to 450 and Simple Endoscopic Score for Crohn’s disease (SES-CD) ≥6 (or ≥4 for isolated ileal disease). Subjects with inadequate response, loss of response, or intolerance to oral aminosalicylates, corticosteroids, immunosuppressants, and/or biologic therapy were enrolled.

At baseline, the median CDAI was 307 (range: 76 – 634) and 307 (range: 72 – 651), and the median SES-CD was 12 (range: 4 – 45) and 13 (range 4 – 40), in CD-1 and CD-2, respectively. In CD-1, 58% (491/850) of subjects had failed or were intolerant to treatment with one or more biologic therapies (prior biologic failure). All subjects in CD-2 had prior biologic failure. At baseline, 30% and 34% of patients were receiving corticosteroids, 24% and 23% of patients were receiving immunomodulators (azathioprine, 6-mercaptopurine, methotrexate), and 31% and 19% of patients were receiving aminosalicylates in CD-1 and CD-2, respectively. In CD-1 and CD-2 combined, the median age was 36 years (ranging from 16 to 80 years), 81% (1145/1419) of subjects were white, and 53% (753/1419) were male.

In CD-1 and CD-2, the co-primary endpoints were clinical remission and endoscopic response at Week 12. Secondary endpoints included clinical response and endoscopic remission (see Table 10 and Table 11). The SKYRIZI 1,200 mg dosage did not demonstrate additional treatment benefit over the 600 mg dosage and is not a recommended regimen [see Dosage and Administration (2.6)].

Table 10. Proportion of Subjects Meeting Efficacy Endpoints at Week 12 – Study CD-1
Endpoint | Placebo | SKYRIZI 600 mg Intravenous Infusiona | Treatment Difference b (95% CI)
Clinical Remissionc,d
Total Population | N=175 25% | N=336 45% | 21% e (12%, 29%)
Prior biologic failuref | N=97 26% | N=195 42%
Without prior biologic failure | N=78 23% | N=141 49%
Endoscopic Responsec, g
Total Population | N=175 12% | N=336 40% | 28% e (21%, 35%)
Prior biologic failuref | N=97 11% | N=195 33%
Without prior biologic failure | N=78 13% | N=141 50%
Clinical Responseh
Total Population | N=175 37% | N=336 60% | 23% e (14%, 32%)
Prior biologic failuref | N=97 34% | N=195 58%
Without prior biologic failure | N=78 40% | N=141 62%
Endoscopic Remissioni
Total Population | N=175 9% | N=336 24% | 15% e (9%, 21%)
Prior biologic failuref | N=97 5% | N=195 18%
Without prior biologic failure | N=78 14% | N=141 32%
a. SKYRIZI 600 mg as an intravenous infusion at Week 0, Week 4, and Week 8
b. Adjusted treatment difference (95% CI) based on Cochran-Mantel-Haenszel method adjusted for randomization stratification factors
c. Co-primary endpoints
d. CDAI <150
e. p <0.001
f. Prior biologic failure includes inadequate response, loss of response, or intolerance to one or more biologic treatments for CD
g. A decrease in SES-CD > 50% from baseline, or a decrease of at least 2 points for subjects with a baseline score of 4 and isolated ileal disease, based on central reading
h. A reduction of CDAI ≥ 100 points from baseline
i. SES-CD ≤ 4 and at least a 2-point reduction from baseline, with no individual subscore greater than 1, based on central reading

Table 11. Proportion of Subjects Meeting Efficacy Endpoints at Week 12 – Study CD-2a
Endpoint | Placebo N=187 | SKYRIZI 600 mg Intravenous Infusionb N=191 | Treatment Differencec (95% CI)
Clinical Remissiond, e | 20% | 42% | 22% f (13%, 31%)
Endoscopic Response d,g | 11% | 29% | 18% f (10%, 25%)
Clinical Responseh | 30% | 60% | 29% f (20%, 39%)
Endoscopic Remissioni | 4% | 19% | 15% f (9%, 21%)
a. All subjects enrolled in CD-2 had prior biologic failure. Prior biologic failure includes inadequate response, loss of response, or intolerance to one or more biologic treatments for CD
b. SKYRIZI 600 mg as an intravenous infusion at Week 0, Week 4, and Week 8
c. Adjusted treatment difference (95% CI) based on Cochran-Mantel-Haenszel method adjusted for randomization stratification factors
d. Co-primary endpoints
e. CDAI score <150
f. p < 0.001
g. A decrease in SES-CD > 50% from baseline, or a decrease of at least 2 points for subjects with a baseline score of 4 and isolated ileal disease, based on central reading
h. A reduction of CDAI ≥ 100 points from baseline
i. SES-CD ≤ 4 and at least a 2-point reduction versus from baseline, with and no individual subscore greater than 1, based on central reading

Onset of clinical response and clinical remission based on CDAI occurred as early as Week 4 in a greater proportion of subjects treated with the SKYRIZI 600 mg induction regimen compared to placebo.

Reductions in stool frequency and abdominal pain were observed in a greater proportion of subjects treated with the SKYRIZI 600 mg induction regimen compared to placebo at Week 12.

Study CD-3

The maintenance study CD-3 evaluated 382 subjects who achieved clinical response defined as a reduction in CDAI of at least 100 points from baseline after 12 weeks of induction treatment with intravenous SKYRIZI in studies CD-1 and CD-2. Subjects were randomized to receive a maintenance regimen of SKYRIZI 180 mg or SKYRIZI 360 mg or placebo at Week 12 and every 8 weeks thereafter for up to an additional 52 weeks.

The co-primary endpoints in CD-3 were clinical remission and endoscopic response at Week 52 (see Table 12).

Table 12. Proportion of Subjects Meeting Efficacy Endpoints at Week 52 - Study CD-3
Endpoint | Placeboa | SKYRIZI 180 mg Subcutaneous Injectionb | SKYRIZI 360 mg Subcutaneous Injectionc | Treatment Difference vs Placebod (95% CI)
 |  |  | SKYRIZI 180 mg | SKYRIZI 360 mg
Clinical Remissione,f
Total Population | N=130 46% | N=135 61% | N=117 57% | 17%g (6%, 28%) |  | 14%g (3%, 26%)
Prior biologic failureh | N=99 40% | N=95 56% | N=83 51%
Without prior biologic failure | N=31 65% | N=40 75% | N=34 71%
Endoscopic Responsee,i
Total Population | N=130 22% | N=135 50% | N=117 48% | 30%g (20%, 39%) | 31%g (21%, 41%)
Prior biologic failureh | N=99 21% | N=95 44% | N=83 44%
Without prior biologic failure | N=31 23% | N=40 65% | N=34 59%
a. The placebo group consisted of patients who were in response to SKYRIZI and were randomized to receive placebo at the start of maintenance therapy.
b. SKYRIZI 180 mg at Week 12 and every 8 weeks thereafter for up to an additional 52 weeks
c. SKYRIZI 360 mg at Week 12 and every 8 weeks thereafter for up to an additional 52 weeks
d. Adjusted treatment difference and 95% CI computed using Cochran-Mantel-Haenszel method adjusted for randomization stratification factors
e. Co-primary endpoints
f. CDAI <150
g. p <0.05
h. Prior biologic failure includes inadequate response, loss of response, or intolerance to one or more biologic treatments for CD
i. A decrease in SES-CD > 50% from baseline, or a decrease of at least 2 points for subjects with a baseline score of 4 and isolated ileal disease, based on central reading

Endoscopic remission was observed at Week 52 in 33% (44/135) of subjects treated with the SKYRIZI 180 mg maintenance regimen and 41% (48/117) of subjects treated with the SKYRIZI 360 mg maintenance regimen, compared to 13% (17/130) of subjects treated with placebo. This endpoint was not statistically significant under the prespecified multiple testing procedure.

14.4 Ulcerative Colitis

Induction Trial (Study UC-1)

In the 12-week induction study (UC-1; NCT03398148), 966 subjects with moderately to severely active ulcerative colitis were randomized and received SKYRIZI 1,200 mg or placebo as an intravenous infusion at Week 0, Week 4, and Week 8. Disease activity was assessed by the modified Mayo score (mMS), a 3-component Mayo score (0-9) which consists of the following subscores (0 to 3 for each subscore): stool frequency (SFS), rectal bleeding (RBS), and findings on centrally read endoscopy score (ES). An ES of 2 was defined by marked erythema, lack of vascular pattern, any friability, and/or erosions; an ES of 3 was defined by spontaneous bleeding and ulceration. Enrolled subjects had a mMS between 5 and 9, with an ES of 2 or 3. Subjects with inadequate response, or intolerance to oral aminosalicylates, corticosteroids, immunomodulators, biologics, Janus Kinase inhibitors (JAKi), and/or sphingosine-1-phosphate receptor modulators (S1PRM) were enrolled.

At baseline in UC-1, the median mMS was 7; 37% had severely active disease (mMS >7); 69% had an ES of 3. In UC-1, 52% (499/966) of subjects had failed (inadequate response or intolerance) treatment with one or more biologics, JAKi or S1PRM. Of these 499 subjects, 484 (97%) failed biologics and 90 (18%) failed JAK inhibitors. Enrolled subjects were permitted to use a stable dose of oral corticosteroids (up to 20 mg/day prednisone or equivalent), immunomodulators, and aminosalicylates. At baseline, 36% of subjects were receiving corticosteroids, 16% of subjects were receiving immunomodulators (including azathioprine, 6-mercaptopurine, methotrexate), and 73% of subjects were receiving aminosalicylates in UC-1.

In UC-1, the primary endpoint was clinical remission defined using the mMS at Week 12 (see Table 13). Key secondary endpoints included clinical response, endoscopic improvement, and histologic endoscopic mucosal improvement (see Table 13).

Table 13. Proportion of Subjects Meeting Efficacy Endpoints at Week 12 – Study UC-1
Endpoint | Placebo | SKYRIZI 1,200 mg Intravenous Infusiona | Treatment Difference (95% CI) b
Clinical Remissionc
Total Population | N=320 8% | N=646 24% | 16%h (12%, 20%)
Prior biologic, JAKi, or S1PRM failured | N=168 6% | N=331 14%
Without prior biologic, JAKi, or S1PRM failure | N=152 9% | N=315 33%
Clinical Responsee
Total Population | N=320 36% | N=646 65% | 29%h (23%, 35%)
Prior biologic, JAKi, or S1PRM failured | N=168 32% | N=331 56%
Without prior biologic, JAKi, or S1PRM failure | N=152 41% | N=315 75%
Endoscopic Improvementf
Total Population | N=320 12% | N=646 36% | 25%h (20%, 30%)
Prior biologic, JAKi, or S1PRM failured | N=168 10% | N=331 26%
Without prior biologic, JAKi, or S1PRM failure | N=152 14% | N=315 47%
Histologic Endoscopic Mucosal Improvement (HEMI) g
Total Population | N=320 7% | N=646 24% | 17%h (13%, 21%)
Prior biologic, JAKi, or S1PRM failured | N=168 7% | N=331 16%
Without prior biologic, JAKi, or S1PRM failure | N=152 8% | N=315 33%
a SKYRIZI 1,200 mg as an intravenous infusion at Week 0, Week 4, and Week 8
b Adjusted treatment difference (95% CI) based on Cochran-Mantel-Haenszel method adjusted for stratification factors
c Per mMS: SFS ≤ 1 and not greater than baseline, RBS = 0, and ES ≤ 1 without friability
d Prior failure includes inadequate response or intolerance to treatment with one or more of the following: biologic therapies, Janus Kinase inhibitors (JAKi), and/or sphingosine-1-phosphate receptor modulators (S1PRM)
e Per mMS: decrease ≥ 2 points and ≥ 30% from baseline, and a decrease in RBS ≥ 1 from baseline or an absolute RBS ≤ 1
f ES ≤ 1 without the evidence of friability
g ES ≤ 1 without the evidence of friability and Geboes score ≤ 3.1 (indicating neutrophil infiltration in <5% of crypts, no crypt destruction and no erosions, ulcerations or granulation tissue)
h p < 0.001

UC-1 was not designed to evaluate the relationship of histologic endoscopic mucosal improvement at week 12 to disease progression and long-term outcomes.

Rectal Bleeding and Stool Frequency Subscores

Decreases in rectal bleeding and stool frequency subscores in subjects treated with SKYRIZI compared to placebo were observed as early as 4 weeks.

Endoscopic Assessment

Endoscopic remission was defined as ES of 0. At Week 12, a greater proportion of subjects treated with SKYRIZI compared to placebo achieved endoscopic remission (11% vs 3%).

Bowel Urgency

A greater proportion of subjects treated with the SKYRIZI 1,200 mg induction regimen compared to placebo had no bowel urgency (44% vs 27%) at Week 12.

Fatigue

In UC-1, subjects treated with SKYRIZI experienced a clinically meaningful improvement in fatigue, assessed by change from baseline in FACIT-F score, at Week 12, compared to placebo-treated subjects. The effect of SKYRIZI to improve fatigue after 12 weeks of induction has not been established.

Other UC Symptoms

The proportion of subjects who had no nocturnal bowel movements was greater in subjects treated with SKYRIZI compared to placebo at Week 12 (67% vs 43%).

Maintenance Study UC-2

The maintenance study (UC-2; NCT03398135) evaluated 547 subjects who received one of three SKYRIZI induction regimens, including the 1,200 mg regimen, for 12 weeks in Studies UC-1 or UC-3 and demonstrated clinical response per mMS after 12 weeks. Subjects were randomized to receive a maintenance regimen of subcutaneous (SC) SKYRIZI 180 mg or SKYRIZI 360 mg or placebo at Week 12 and every 8 weeks thereafter for up to an additional 52 weeks.

In UC-2, 75% (411/547) of subjects had failed (inadequate response or intolerance) treatment with one or more biologics, JAKi, or S1PRM. Of these 411 subjects, 407 (99%) failed biologics and 78 (19%) failed JAK inhibitors.

The primary endpoint in UC-2 was clinical remission using mMS at Week 52 (see Table 14). Key secondary endpoints included corticosteroid-free clinical remission, endoscopic improvement, and histologic endoscopic mucosal improvement (see Table 14).

Table 14. Proportion of Subjects Meeting Efficacy Endpoints at Week 52 - Study UC-2
Endpoint | Placeboa | SKYRIZI 180 mg SC Injectionb | SKYRIZI 360 mg SC Injectionc
Clinical remissiond
Total Population | N=182 26% | N=179 45% | N=186 41%
Treatment Difference vs Placeboe (95% CI) |  | 20% j [11%, 29%] | 16% j [7%, 25%]
Prior biologic, JAKi, or S1PRM failuref | N=138 24% | N=134 41% | N=139 32%
Without prior biologic, JAKi, or S1PRM failure | N=44 32% | N=45 58% | N=47 67%
Corticosteroid-free clinical remissiong
Total Population | N=182 26% | N=179 45% | N=186 40%
Treatment Difference vs Placeboe (95% CI) |  | 20% j [11%, 29%] | 16%j [7%, 25%]
Prior biologic, JAKi, or S1PRM failuref | N=138 24% | N=134 40% | N=139 32%
Without prior biologic, JAKi, or S1PRM failure | N=44 32% | N=45 58% | N=47 64%
Endoscopic improvementh
Total Population | N=182 31% | N=179 51% | N=186 48%
Treatment Difference vs Placeboe (95% CI) |  | 20% j [11%, 30%] | 18% j [8%, 27%]
Prior biologic, JAKi, or S1PRM failuref | N=138 30% | N=134 48% | N=139 39%
Without prior biologic, JAKi, or S1PRM failure | N=44 34% | N=45 60% | N=47 76%
Histologic Endoscopic Mucosal Improvementi
Total Population | N=182 24% | N=179 43% | N=186 42%
Treatment Difference vs Placeboe (95% CI) |  | 20% j [11%, 29%] | 20% j [11%, 29%]
Prior biologic, JAKi, or S1PRM failuref | N=138 22% | N=134 39% | N=139 33%
Without prior biologic, JAKi, or S1PRM failure | N=44 30% | N=45 55% | N=47 69%
a The placebo group consisted of subjects who were in response to 12 weeks of SKYRIZI induction and were randomized to receive placebo at the start of maintenance therapy.
b SKYRIZI 180 mg at Week 12 and every 8 weeks thereafter for up to an additional 52 weeks
c SKYRIZI 360 mg at Week 12 and every 8 weeks thereafter for up to an additional 52 weeks
d Per mMS: SFS ≤ 1 and not greater than baseline, RBS = 0, and ES ≤ 1 without friability
e Adjusted treatment difference (95% CI) based on Cochran-Mantel-Haenszel method adjusted for stratification factors
f Prior failure includes inadequate response or intolerance to treatment with one or more of the following: biologic therapies, Janus Kinase inhibitors (JAKi), and/or sphingosine-1-phosphate receptor modulators (S1PRM)
g Clinical remission per mMS at Week 52 and corticosteroid-free for ≥90 days
h ES ≤ 1 without the evidence of friability
i ES ≤ 1without the evidence of friability and Geboes score ≤ 3.1 (indicating neutrophil infiltration in <5% of crypts, no crypt destruction and no erosions, ulcerations or granulation tissue)
j p < 0.001

Endoscopic Assessment

Endoscopic remission was defined as ES of 0. In UC-2, a greater proportion of subjects treated with SKYRIZI 180 mg and SKYRIZI 360 mg compared to placebo achieved endoscopic remission at Week 52 (23% and 24% vs 15%).

16 HOW SUPPLIED/STORAGE AND HANDLING

How Supplied

SKYRIZI (risankizumab-rzaa) injection is supplied in the following strengths:

Strength | Pack Size | NDC
Subcutaneous Injection
150 mg/mL single-dose pen | Carton of 1 | 0074-2100-01
90 mg/mL single-dose prefilled syringe | Carton of 2 | 0074-7040-02
 | Carton of 4 | 0074-7042-04
180 mg/1.2 mL (150 mg/mL) single-dose prefilled syringe | Carton of 1 | 0074-8300-01
 | Carton of 2 | 0074-8350-01
150 mg/mL single-dose prefilled syringe | Carton of 1 | 0074-1050-01
180 mg/1.2 mL (150 mg/mL) single-dose prefilled cartridge with on-body injector | Kit | 0074-1065-01
360 mg/2.4 mL (150 mg/mL) single-dose prefilled cartridge with on-body injector | Kit | 0074-1070-01
Intravenous Infusion
600 mg/10 mL (60 mg/mL) single-dose vial | Carton of 1 | 0074-5015-01

Subcutaneous Injection

SKYRIZI 150 mg/mL prefilled syringe or prefilled pen contains a sterile, preservative-free, colorless to yellow, and clear to slightly opalescent solution. Each prefilled syringe or prefilled pen consists of a 1 mL glass syringe with a fixed 27-gauge ½ inch needle with needle guard.

SKYRIZI 90 mg/mL prefilled syringe contains a sterile, preservative-free, colorless to slightly yellow and clear to slightly opalescent solution. Each prefilled syringe consists of a 1 mL glass syringe with a fixed 29-gauge ½ inch needle with needle guard.

SKYRIZI 180 mg/1.2 mL (150 mg/mL) prefilled syringe contains a sterile, preservative-free, colorless to yellow, and clear to slightly opalescent solution. Each prefilled syringe consists of a 2.25 mL glass syringe with a fixed 27-gauge ½ inch needle with needle guard.

SKYRIZI 180 mg/1.2 mL (150 mg/mL) cyclic olefin polymer prefilled cartridge with a septum and cap contains a sterile, preservative-free, colorless to yellow, and clear to slightly opalescent solution for use with supplied on-body injector administration device.

SKYRIZI 360 mg/2.4 mL (150 mg/mL) cyclic olefin polymer prefilled cartridge with a septum and cap contains a sterile, preservative-free, colorless to yellow, and clear to slightly opalescent solution for use with supplied on-body injector administration device.

Intravenous Infusion

SKYRIZI 600 mg/10 mL (60 mg/mL) vial contains a sterile and preservative-free, colorless to slightly yellow, and clear to slightly opalescent solution. Each glass vial is closed with a stopper and blue flip cap.

Storage and Handling

- Store in a refrigerator at 36°F to 46° F (2°C to 8°C).
- Do not freeze.
- Do not shake.
- Keep in the original cartons to protect from light.
- Not made with natural rubber latex.

17 PATIENT COUNSELING INFORMATION

Advise the patient and/or caregiver to read the FDA-approved patient labeling (Medication Guide and Instructions for Use).

Hypersensitivity Reactions

Advise patients to discontinue SKYRIZI and seek immediate medical attention if they experience any symptoms of serious hypersensitivity reactions [see Warnings and Precautions (5.1)].

Infections

Inform patients that SKYRIZI may lower the ability of their immune system to fight infections. Instruct patients of the importance of communicating any history of infections to the healthcare provider and contacting their healthcare provider if they develop any symptoms of an infection [see Warnings and Precautions (5.2)].

Hepatotoxicity in Treatment of Inflammatory Bowel Disease

Inform patients that SKYRIZI may cause liver injury, especially during the initial 12 weeks of treatment. Instruct patients to seek immediate medical attention if they experience symptoms suggestive of liver dysfunction. (e.g., unexplained rash, nausea, vomiting, abdominal pain, fatigue, anorexia, or jaundice and/or dark urine) [see Warnings and Precautions (5.4)].

Administration of Vaccines

Advise patients that vaccination with live vaccines is not recommended during SKYRIZI treatment and immediately prior to or after SKYRIZI treatment. Medications that interact with the immune system may increase the risk of infection following administration of live vaccines. Instruct patients to inform the healthcare practitioner that they are taking SKYRIZI prior to a potential vaccination [see Warnings and Precautions (5.5)].

Administration Instruction

Instruct patients or caregivers to perform the first self-injected dose under the supervision and guidance of a qualified healthcare professional for training in preparation and administration of SKYRIZI, including choosing anatomical sites for administration, and proper subcutaneous injection technique [see Instructions for Use].

If using SKYRIZI 90 mg/mL, instruct patients or caregivers to administer two 90 mg single-dose syringes to achieve the full 180 mg maintenance dose or four 90 mg single-dose syringes to achieve the full 360 mg maintenance dose of SKYRIZI for Crohn’s disease or ulcerative colitis [see Instructions for Use].

If using SKYRIZI 180 mg/1.2 mL, instruct patients or caregivers to administer one 180 mg single-dose syringe to achieve the full 180 mg maintenance dose or two 180 mg single-dose syringes to achieve the full 360 mg maintenance dose of SKYRIZI for Crohn’s disease or ulcerative colitis [see Instructions for Use].

Instruct patients or caregivers in the technique of pen or syringe disposal [see Instructions for Use].

Pregnancy

Advise patients that there is a pregnancy registry that monitors pregnancy outcomes in women exposed to SKYRIZI during pregnancy [see Use in Specific Populations (8.1)].

Manufactured by:
AbbVie Inc.
North Chicago, IL 60064, USA

US License Number 1889
SKYRIZI® is a registered trademark of AbbVie Biotechnology Ltd.
© 2019-2025 AbbVie Inc.

20087561 9/2025

Medication Guide
SKYRIZI® (sky-RIZZ-ee)
(risankizumab-rzaa)
injection, for subcutaneous or intravenous use

What is the most important information I should know about SKYRIZI?
SKYRIZI may cause serious side effects, including:
Serious allergic reactions. Stop using SKYRIZI and get emergency medical help right away if you get any of the following symptoms of a serious allergic reaction:

● fainting, dizziness, feeling lightheaded (low blood pressure)

● chest tightness

● swelling of your face, eyelids, lips, mouth, tongue, or throat

● skin rash, hives

● trouble breathing or throat tightness

● itching

Infections. SKYRIZI may lower the ability of your immune system to fight infections and may increase your risk of infections. Your healthcare provider should check you for infections and tuberculosis (TB) before starting treatment with SKYRIZI and may treat you for TB before you begin treatment with SKYRIZI if you have a history of TB or have active TB. Your healthcare provider should watch you closely for signs and symptoms of TB during and after treatment with SKYRIZI. Tell your healthcare provider right away if you have an infection or have symptoms of an infection, including:

● fever, sweats, or chills

● muscle aches

● weight loss

● cough

● warm, red, or painful skin or sores on your body different from your psoriasis

● diarrhea or stomach pain

● shortness of breath

● burning when you urinate or urinating more often than normal

● blood in your mucus
(phlegm)

See “What are the possible side effects of SKYRIZI?” for more information about side effects.

What is SKYRIZI?
SKYRIZI is a prescription medicine used to treat:

- moderate to severe plaque psoriasis in adults who may benefit from taking injections or pills (systemic therapy) or treatment using ultraviolet or UV light (phototherapy).
- active psoriatic arthritis in adults.
- moderate to severe Crohn’s disease in adults.
- moderate to severe ulcerative colitis in adults.
  It is not known if SKYRIZI is safe and effective in children.

Who should not use SKYRIZI?
Do not use SKYRIZI if you are allergic to risankizumab-rzaa or any of the ingredients in SKYRIZI. See the end of this Medication Guide for a complete list of ingredients in SKYRIZI.

Before using SKYRIZI, tell your healthcare provider about all of your medical conditions, including if you:

- have any of the conditions or symptoms listed in the section “What is the most important information I should know about SKYRIZI?”
- have an infection that does not go away or that keeps coming back.
- have TB or have been in close contact with someone with TB.
- have recently received or are scheduled to receive an immunization (vaccine). Medicines that interact with the immune system may increase your risk of getting an infection after receiving live vaccines. You should avoid receiving live vaccines right before, during, or right after treatment with SKYRIZI. Tell your healthcare provider that you are taking SKYRIZI before receiving a vaccine.
- are pregnant or plan to become pregnant. It is not known if SKYRIZI can harm your unborn baby.
- are breastfeeding or plan to breastfeed. It is not known if SKYRIZI passes into your breast milk.
- If you become pregnant while taking SKYRIZI, you are encouraged to enroll in the Pregnancy Registry. The purpose of the pregnancy registry is to collect information about the health of you and your baby. Talk to your healthcare provider or call 1-877-302-2161 to enroll in this registry.

Tell your healthcare provider about all the medicines you take, including prescription and over-the-counter medicines, vitamins, and herbal supplements.

How should I use SKYRIZI?
See the detailed “Instructions for Use” that comes with SKYRIZI for information on how to prepare and inject a dose of SKYRIZI, and how to properly throw away (dispose of) a used SKYRIZI prefilled pen, prefilled syringe, or prefilled cartridge with on-body injector.

- Use SKYRIZI exactly as your healthcare provider tells you to use it.
- Your healthcare provider will tell you how much SKYRIZI is right for you and how often you should receive it.
- Before self-injecting with SKYRIZI prefilled pen, prefilled syringe, or prefilled cartridge with on-body injector, your healthcare provider should show you how to inject SKYRIZI.
- If you miss your SKYRIZI dose, inject a dose as soon as you remember. Then, take your next dose at your regular scheduled time. Call your healthcare provider if you are not sure what to do.
- If you inject more SKYRIZI than prescribed, call your healthcare provider right away.

Adults with plaque psoriasis or psoriatic arthritis will receive SKYRIZI as an injection under the skin (subcutaneous injection) using the prefilled pen or prefilled syringe.
Adults with Crohn’s disease or ulcerative colitis will receive their starter doses with SKYRIZI through a vein in the arm (intravenous infusion) in a healthcare facility by a healthcare provider. After completing the starter doses, patients will receive SKYRIZI as 1 or more injections under the skin (subcutaneous injection) using the prefilled cartridge with on-body injector or prefilled syringe.

What are the possible side effects of SKYRIZI?
SKYRIZI may cause serious side effects including:

- See “What is the most important information I should know about SKYRIZI?”
- Liver problems may happen while being treated for Crohn’s disease or ulcerative colitis. A person with Crohn’s disease who received SKYRIZI by intravenous infusion (through a vein in the arm) developed changes in liver blood tests with a rash that led to hospitalization. Your healthcare provider will do blood tests to check your liver before, during, and at least up to 12 weeks of treatment with SKYRIZI. Your healthcare provider may stop treatment with SKYRIZI if you develop liver problems. Tell your healthcare provider right away if you notice any of the following symptoms:

- unexplained rash
- nausea

- vomiting
- stomach (abdominal) pain

- tiredness (fatigue)
- loss of appetite

- yellowing of the skin and eyes (jaundice)
- dark urine

The most common side effects of SKYRIZI in people treated for Crohn’s disease and ulcerative colitis include:

- upper respiratory infections
- headache
- joint pain

- stomach (abdominal) pain
- injection site reactions
- low red blood cells (anemia)

- fever
- back pain
- urinary tract infection
- rash

The most common side effects of SKYRIZI in people treated for plaque psoriasis and psoriatic arthritis include:

- upper respiratory infections
- headache

- feeling tired
- injection site reactions

- fungal skin infections

These are not all the possible side effects of SKYRIZI.
Call your doctor for medical advice about side effects. You may report side effects to FDA at 1-800-FDA-1088.

How should I store SKYRIZI?

- Store SKYRIZI in the refrigerator between 36°F to 46°F (2°C to 8°C).
- Do not freeze SKYRIZI.
- Do not shake SKYRIZI.
- Keep SKYRIZI in the original carton to protect it from light.
- SKYRIZI is not made with natural rubber latex.

Keep SKYRIZI and all medicines out of the reach of children.

General information about the safe and effective use of SKYRIZI.
Medicines are sometimes prescribed for purposes other than those listed in a Medication Guide. Do not use SKYRIZI for a condition for which it was not prescribed. Do not give SKYRIZI to other people, even if they have the same symptoms that you have. It may harm them. You can ask your pharmacist or healthcare provider for information about SKYRIZI that is written for health professionals.

What are the ingredients in SKYRIZI?
Active ingredient: risankizumab-rzaa.
SKYRIZI 90 mg/mL prefilled syringe inactive ingredients: polysorbate 20, sodium succinate, sorbitol, succinic acid, and Water for Injection, USP.
SKYRIZI 150 mg/mL prefilled pen or prefilled syringe, 180 mg/1.2 mL prefilled syringe or prefilled cartridge, 360 mg/2.4 mL prefilled cartridge, and 600 mg/ 10 mL vial inactive ingredients: glacial acetic acid, polysorbate 20, sodium acetate, trehalose, and Water for Injection, USP.
Manufactured by: AbbVie Inc., North Chicago, IL 60064, U.S.A.
US License Number 1889
SKYRIZI® is a registered trademark of AbbVie Biotechnology Ltd.
© 2019-2025 AbbVie Inc.
For more information, call 1-866-SKYRIZI (1-866-759-7494) or go to www.SKYRIZI.com.

This Medication Guide has been approved by the U.S. Food and Drug Administration
20087561

Revised: 9/2025

INSTRUCTIONS FOR USE
SKYRIZI® (sky-RIZZ-ee) Pen
(risankizumab-rzaa)
injection, for subcutaneous use

Read Before First Use

Refer to the Medication Guide for product information.

Read this Instructions for Use before using SKYRIZI Pen (risankizumab-rzaa) injection.

Before using SKYRIZI, you should receive training from your healthcare provider on how to inject SKYRIZI.

SKYRIZI Single-Dose Pen

Important Information

- Store SKYRIZI in the refrigerator at 36°F to 46°F (2°C to 8°C).
- Keep SKYRIZI in the original carton to protect from light until you are ready to use.
- Before injecting, take the SKYRIZI carton out of the refrigerator. Leave the carton at room temperature and out of direct sunlight for 30 to 90 minutes.
- The liquid in the inspection window should look clear to yellow and may contain tiny white or clear particles.
- Do not use SKYRIZI if the liquid is discolored, cloudy or contains flakes or large particles.
- Do not use SKYRIZI if the expiration date (EXP) has passed.
- Do not use SKYRIZI if the liquid has been frozen, even if it has been thawed.
- Do not shake SKYRIZI.
- Do not use if the SKYRIZI Pen has been dropped or damaged.
- Do not use SKYRIZI if carton perforations are broken. Return product to pharmacy.
- Do not remove the dark gray cap until right before injection.
- SKYRIZI is not made with natural rubber latex.

Prepare SKYRIZI injection

Take the SKYRIZI carton out of the refrigerator. Leave the carton at room temperature and out of direct sunlight for 30 to 90 minutes before injecting.

- Do not remove the Pen from the carton while allowing SKYRIZI to reach room temperature.
- Do not warm SKYRIZI in any other way. For example, do not warm it in a microwave or in hot water.
- Do not use the Pen if the liquid has been frozen, even if it has been thawed.

Check expiration date (EXP). Do not use the Pen if expiration date has passed.
Place the following on a clean, flat surface:

- 1 single-dose SKYRIZI Pen (included)
- 1 alcohol swab (not included)
- 1 cotton ball or gauze pad (not included)
- FDA-cleared sharps disposal container (not included). See “Used SKYRIZI Prefilled Pen Disposal” for information on how to throw away (dispose of) used Pens.

Wash and dry your hands.

Choose an injection site:

- on the front of your thighs or
- your abdomen (belly) at least 2 inches from your navel (belly button)

Wipe the injection site in a circular motion with the alcohol swab and let it dry.

- Do not touch or blow on the injection site after it is cleaned. Allow the skin to dry before injecting.
- Do not inject through clothes.
- Do not inject into skin that is sore, bruised, red, hard, scarred, has stretch marks, or areas with psoriasis.

Hold the Pen with the dark gray cap pointing up.

- Pull the dark gray cap straight off.
- Throw the dark gray cap away.

Check the liquid through the inspection window.

- It is normal to see 1 or more bubbles in the liquid.
- The liquid should look clear to yellow and may contain tiny white or clear particles.
- Do not use if the liquid is discolored, cloudy or contains flakes or large particles.

Give SKYRIZI injection

Hold the Pen with your fingers on the gray hand grips.
Turn the Pen so that the white needle sleeve points toward the injection site and you can see the green activator button.
Pinch the skin at your injection site to make a raised area and hold it firmly.
Place the white needle sleeve straight (90-degree angle) against the raised injection site.

Hold the Pen so that you can see the green activator button and inspection window.
Push and keep pressing the Pen down against the raised injection site.

- The Pen will activate only if the white needle sleeve is pressed down against the injection site before pressing the green activator button.

Press the green activator button and hold the Pen for 15 seconds.

- The first loud “click” means the start of the injection.

Keep pressing the Pen down against the injection site.
The injection is complete when:

- the Pen has made a second “click” or
- the yellow indicator has filled the inspection window

This takes up to 15 seconds.

After SKYRIZI injection

When the injection is complete, slowly pull the Pen straight out from the skin.
The white needle sleeve will cover the needle tip and make another “click.”
After completing the injection, place a cotton ball or gauze pad on the skin at the injection site.

- Do not rub the injection site.
- Slight bleeding at the injection site is normal.

Throw away (dispose of) the used Pen in a FDA-cleared sharps disposal container right away after use.
● Do not dispose of used Pens in your household trash unless your community guidelines permit this.
● Do not recycle your sharps disposal container.
The dark gray cap, alcohol swab, cotton ball or gauze pad, and packaging may be placed in your household trash.
For more information, see “Used SKYRIZI Prefilled Pen Disposal”.

Important Information

- Store SKYRIZI in the refrigerator at 36°F to 46°F (2°C to 8°C).
- Keep SKYRIZI in the original carton to protect from light until you are ready to use.
- Before injecting, take the SKYRIZI carton out of the refrigerator. Leave the carton at room temperature and out of direct sunlight for 30 to 90 minutes.
- The liquid in the inspection window should look clear to yellow and may contain tiny white or clear particles.
- Do not use SKYRIZI if the liquid is discolored, cloudy or contains flakes or large particles.
- Do not use SKYRIZI if the expiration date (EXP) has passed.
- Do not use SKYRIZI if the liquid has been frozen, even if it has been thawed.
- Do not shake SKYRIZI.
- Do not use if the SKYRIZI Pen has been dropped or damaged.
- Do not use SKYRIZI if carton perforations are broken. Return product to pharmacy.
- Do not remove the dark gray cap until right before injection.
- SKYRIZI is not made with natural rubber latex.

Keep the SKYRIZI Pen and sharps disposal container out of the reach of children.

Call your healthcare provider or (866) SKYRIZI or (866) 759-7494 if you need help or do not know how to proceed.

Questions About Using the SKYRIZI Pen

Q. What if I need help on how to inject SKYRIZI?

A. Call your healthcare provider or (866) SKYRIZI or (866) 759-7494 if you need help.

Q. I have removed the dark gray cap and pressed the green activator button. Why isn’t my injection starting?

A. The green activator button will not start the injection unless the white needle sleeve is pressed firmly against the injection site.

Q. How do I know when the injection is complete?

A. The injection is complete if the Pen makes a second “click” or the yellow indicator fills the inspection window. This takes up to 15 seconds.

Q. What should I do if there are more than a few drops of liquid on the injection site?

A. Call (866) SKYRIZI or (866) 759-7494 for help.

Q. What should I do with the used Pen after my injection?

A. Dispose of the used Pen in a sharps disposal container right after use. Do not dispose of the used Pen in your household trash.

You can sign up to receive sharps containers for SKYRIZI Pen disposal at no additional cost by going to www. SKYRIZI.com or calling (866) SKYRIZI or (866) 759-7494.

Call (866) SKYRIZI or (866) 759-7494 or go to www. SKYRIZI.com for help with your injection.

To help remember when to inject, mark your calendar with the date you give your SKYRIZI injection.

Keep the SKYRIZI Pen and sharps disposal container out of the reach of children.

Call your healthcare provider or (866) SKYRIZI or (866) 759-7494 if you need help or have questions about the use of SKYRIZI.

Used SKYRIZI Prefilled Pen Disposal

If you do not have a FDA-cleared sharps disposal container, you may use a household container that is:

- made of a heavy-duty plastic,
- can be closed with a tight-fitting, puncture-resistant lid, without sharps being able to come out,
- upright and stable during use,
- leak-resistant, and
- properly labeled to warn of hazardous waste inside the container.

When your sharps disposal container is almost full, you will need to follow your community guidelines for the right way to dispose of your sharps disposal container. There may be state or local laws about how you should throw away used Pens.

For more information about safe sharps disposal, and for specific information about sharps disposal in the state that you live in, go to the FDA’s website at: www.fda.gov/safesharpsdisposal.

Do not recycle your used sharps disposal container.

Manufactured by: AbbVie Inc., North Chicago, IL 60064, U.S.A.
US License Number 1889
SKYRIZI® is a registered trademark of AbbVie Biotechnology Ltd.
© 2019-2024 AbbVie Inc.
20086179

This Instructions for Use has been approved by the U.S. Food and Drug Administration.

Revised: 6/2024

INSTRUCTIONS FOR USE
SKYRIZI® (sky-RIZZ-ee)
(risankizumab-rzaa)
injection, for subcutaneous use
150 mg/mL prefilled syringe

Read Before First Use

Refer to the Medication Guide for product information.

SKYRIZI Single-Dose Prefilled Syringe

Important Information

- Keep SKYRIZI in the original carton to protect from light until time to use.
- The liquid should look clear to yellow and may contain tiny white or clear particles.
- Do not use SKYRIZI if the liquid is discolored, cloudy or contains flakes or large particles.
- Do not use SKYRIZI if the expiration date (EXP:) shown on the carton and prefilled syringe has passed.
- Do not use SKYRIZI if the liquid has been frozen (even if thawed).
- Do not shake SKYRIZI.
- Do not use SKYRIZI if the prefilled syringe has been dropped or damaged.
- Do not use SKYRIZI if carton perforations are broken. Return product to the pharmacy.
- Do not remove the needle cover until right before giving the injection.

Keep SKYRIZI and all medicines out of the reach of children.

Please Read Complete Instructions for Use Before Using SKYRIZI Prefilled Syringe

Before Injecting

- Receive training on how to inject SKYRIZI before giving injection. Call your healthcare provider or (866) SKYRIZI or (866) 759-7494 if you need help.
- Mark your calendar ahead of time to remember when to take SKYRIZI.
- Leave the carton at room temperature and out of direct sunlight for 15 to 30 minutes to warm.
  - Do not remove the syringe from the carton while allowing SKYRIZI to reach room temperature.
  - Do not warm SKYRIZI in any other way (for example, do not warm it in a microwave or in hot water).

Important Information

- The liquid should look clear to yellow and may contain tiny white or clear particles.
- Do not use SKYRIZI if the liquid is discolored, cloudy or contains flakes or large particles.
- Do not use SKYRIZI if the expiration date (EXP:) shown on the carton and prefilled syringe has passed.
- Do not use SKYRIZI if the syringe has been dropped or damaged.
- Do not use SKYRIZI if carton perforations are broken. Return product to the pharmacy.

Storage Information

- Store SKYRIZI in the refrigerator between 36°F to 46°F (2°C to 8°C).
- Do not shake SKYRIZI.
- Keep SKYRIZI in the original carton to protect from light until time to use.
- SKYRIZI is not made with natural rubber latex.
- Do not use if the liquid has been frozen (even if thawed).

Keep SKYRIZI and all medicines out of the reach of children.

Call your healthcare provider or (866) SKYRIZI or (866) 759-7494 if you need help or do not know how to proceed.

Gather the supplies for the injection.

- Do not hold or pull the plunger rod when removing the prefilled syringe from the sleeve.

Place the following on a clean, flat surface:

- 1 prefilled syringe (included)
- 1 alcohol swab (not included)
- 1 cotton ball or gauze pad (not included)
- FDA-cleared sharps disposal container (not included). See “Used SKYRIZI Prefilled Syringe Disposal” for information on how to throw away (dispose of) used prefilled syringes.

Wash and dry your hands.

Remove prefilled syringe from cardboard sleeve by holding the finger grip.

Pick from the 3 injectable areas:

- Front of left thigh or right thigh
- Your abdomen (belly) at least 2 inches from your navel (belly button)

Wipe the injection site in a circular motion with the alcohol swab before the injection.

- Do not touch or blow on the injection site after it is cleaned. Allow the skin to dry before injecting.
- Do not inject through clothes.
- Do not inject into skin that is sore, bruised, red, hard, scarred, or has stretch marks, or into areas affected by psoriasis.

Hold the prefilled syringe with covered needle facing down, as shown.
Check the liquid in the prefilled syringe.

- It is normal to see 1 or more bubbles in the window.
- The liquid should look clear to yellow and may contain tiny white or clear particles.
- Do not use the prefilled syringe if the liquid is discolored, cloudy or contains flakes or large particles.

Remove the needle cover.

- Hold the prefilled syringe in 1 hand between the finger grip and needle cover.
- With the other hand, gently pull the needle cover straight off.
- Do not hold or pull the plunger rod when removing the needle cover.
- You may see a drop of liquid at the end of the needle. This is normal.
- Throw away the needle cover.
- Do not touch the needle with your fingers or let the needle touch anything.

Hold the body of the prefilled syringe in 1 hand between the thumb and index fingers.
Pinch the area of cleaned skin with your other hand and hold it firmly.
Insert the needle into the skin at about a 45-degree angle using a quick, short movement. Hold angle steady.

Slowly push the plunger rod all the way in until all of the liquid is injected, and the prefilled syringe is empty.
Pull the needle out of the skin while keeping the prefilled syringe at the same angle.
Release the plunger rod and allow the prefilled syringe to move up until the entire needle is covered by the needle guard.
The prefilled syringe needle guard will not activate unless all the liquid has been injected.

- Press a cotton ball or gauze pad over the injection site and hold for 10 seconds.
- Do not rub the injection site. You may have slight bleeding. This is normal.

Put your used prefilled syringe in a FDA-cleared sharps disposal container right away after use.

- Do not throw away (dispose of) the used prefilled syringe in the household trash.

For more information, see “Used SKYRIZI Prefilled Syringe Disposal” section.

Questions About Using SKYRIZI

Q. What if I need help on how to inject SKYRIZI?

A. Call your healthcare provider or (866) SKYRIZI or (866) 759-7494 if you need help.

Q. What should I do with the used prefilled syringe after my injection?

A. Throw away (dispose of) the used prefilled syringe in a sharps disposal container and not your household trash.
You can sign up to receive sharps containers for SKYRIZI syringe disposal at no additional cost by going to www.SKYRIZI.com or calling (866) SKYRIZI or (866) 759-7494.

Q. How do I know when the injection is complete?

A. The injection is complete when the prefilled syringe is empty, the plunger rod is pushed all the way in, and the syringe needle guard is activated.

Used SKYRIZI Prefilled Syringe Disposal

If you do not have a FDA-cleared sharps disposal container, you may use a household container that is:

- made of a heavy-duty plastic,
- can be closed with a tight-fitting, puncture-resistant lid, without sharps being able to come out,
- upright and stable during use,
- leak-resistant, and
- properly labeled to warn of hazardous waste inside the container.

When your sharps disposal container is almost full, you will need to follow your community guidelines for the right way to dispose of your sharps disposal container. There may be state or local laws about how you should throw away used needles and syringes.

For more information about safe sharps disposal, and for specific information about sharps disposal in the state that you live in, go to the FDA’s website at: www.fda.gov/safesharpsdisposal.

Do not recycle your used sharps disposal container.

Manufactured by: AbbVie Inc., North Chicago, IL 60064, U.S.A.
US License Number 1889
SKYRIZI® is a registered trademark of AbbVie Biotechnology Ltd.
© 2019-2024 AbbVie Inc.
20086082

This Instructions for Use has been approved by the U.S. Food and Drug Administration.

Revised: 6/2024

Instructions for Use
SKYRIZI® (sky-RIZZ-ee)
(risankizumab-rzaa)
injection, for subcutaneous use

2 x 90 mg/mL single-dose prefilled syringes for a total 180 mg/2 mL dose

Read Before First Use

Refer to the Medication Guide for product information.

SKYRIZI Single-Dose Prefilled Syringe

Keep SKYRIZI and all medicines out of the reach of children.

Important Information:

- Keep SKYRIZI in the original carton to protect from light until time to use.
- The liquid should look clear to slightly yellow and may contain tiny white or clear particles.
- Do not use SKYRIZI if the liquid is discolored, cloudy or contains flakes or large particles. Return product to pharmacy.
- Do not use SKYRIZI if the expiration date (EXP:) shown on the carton and prefilled syringe has passed. Return product to pharmacy.
- Do not use SKYRIZI if the liquid has been frozen (even if thawed).
- Do not shake the syringe.
- Do not use SKYRIZI if the prefilled syringe has been dropped or damaged. Return product to pharmacy.
- Do not use SKYRIZI if carton perforations are broken. Return product to the pharmacy.
- Do not remove the needle cover until right before giving the injections.
- SKYRIZI is not made with natural rubber latex.

Please Read Complete Instructions for Use Before Using SKYRIZI Prefilled Syringe

Before Injecting:

- Receive training on how to inject SKYRIZI before giving injections. Call your healthcare provider or (866) SKYRIZI or (866) 759-7494 if you need help.
- Mark your calendar ahead of time to remember when to take SKYRIZI.
- Leave the carton at room temperature and out of direct sunlight for 15 to 30 minutes to warm.
  - Do not remove the prefilled syringes from the carton while allowing SKYRIZI to reach room temperature.
  - Do not warm SKYRIZI in any other way (for example, do not warm it in a microwave or in hot water).

Important Information:

- The liquid should look clear to slightly yellow and may contain tiny white or clear particles.
- Do not use SKYRIZI if the liquid is discolored, cloudy or contains flakes or large particles. Return product to pharmacy.
- Do not use SKYRIZI if the expiration date (EXP:) shown on the carton and prefilled syringe has passed. Return product to pharmacy.
- Do not use SKYRIZI if the prefilled syringe has been dropped or damaged. Return product to pharmacy.
- Do not use SKYRIZI if carton perforations are broken. Return product to pharmacy.

Storage Information:

- Store SKYRIZI in the refrigerator between 36°F to 46°F (2°C to 8°C).
- Do not shake SKYRIZI.
- Keep SKYRIZI in the original carton to protect from light until time to use.
- SKYRIZI is not made with natural rubber latex.
- Do not use if liquid has been frozen (even if thawed).

Keep SKYRIZI and all medicines out of the reach of children.

Call your healthcare provider or (866) SKYRIZI or (866) 759-7494 if you need help or do not know how to proceed.

Gather the supplies for the injections and place the following on a clean, flat surface:

- 2 prefilled syringes
- 2 alcohol swabs and 2 cotton balls or gauze pads (not included)
- FDA-cleared sharps disposal container (not included) See “Used SKYRIZI Prefilled Syringe Disposal” for information on how to throw away (dispose of) used prefilled syringes.

Wash and dry your hands.
Start with 1 prefilled syringe for first injection.

Pick from the 3 injectable areas:

- Front of left thigh or right thigh
- Your abdomen (belly) at least 2 inches from your navel (belly button)

Wipe the injection site in a circular motion with the alcohol swab (before both injections)

- Do not touch or blow on the injection site after it is cleaned. Allow the skin to dry before injecting.
- Do not inject through clothes.
- Do not inject into skin that is sore, bruised, red, hard, scarred, or has stretch marks.

Hold the prefilled syringe with covered needle facing down, as shown.
Check the liquid in the prefilled syringe.

- It is normal to see one or more bubbles in the window.
- The liquid should look clear to slightly yellow and may contain tiny white or clear particles.
- Do not use the prefilled syringe if liquid is discolored, cloudy or contains flakes or large particles.

Remove the needle cover.

- Do not hold or pull plunger rod when removing the needle cover.
- Hold the syringe in 1 hand between the finger grip and needle cover.
- With the other hand, carefully pull the needle cover straight off.
- You may see a drop of liquid at the end of the needle. This is normal.
- Throw away the needle cover.
- Do not touch the needle with your fingers or let the needle touch anything.

Hold the body of the prefilled syringe in 1 hand between the thumb and index finger.
Gently pinch the area of cleaned skin with your other hand and hold it firmly.
Insert the needle into the skin at about a 45-degree angle using a quick, short movement. Hold angle steady.

Slowly push the plunger rod all the way in until all of the liquid is injected and the syringe is empty.
Pull the needle out of the skin while keeping the syringe at the same angle.
Release the plunger rod.

- Allow the prefilled syringe to move up until the entire needle is covered by the needle guard.

The needle guard will not automatically activate unless all the liquid has been injected.

- Press a cotton ball or gauze pad over the injection site and hold for 10 seconds.
- Do not rub the injection site. You may have slight bleeding. This is normal.

Repeat Steps 2 through 6 with the 2nd prefilled syringe for a full dose.

- Use the 2nd prefilled syringe right after using the 1st syringe.

Put your used prefilled syringes in an FDA-cleared sharps disposal container right away after use.

- Do not throw away (dispose of) used prefilled syringes in the household trash.

For more information, or if you do not have an FDA-cleared sharps container see “Used SKYRIZI Prefilled Syringe Disposal” section located on the other side of these instructions.

Questions About Using the SKYRIZI Syringe

Q. What if I have not received in-person training from a healthcare professional?

A. Call your healthcare provider or (866) SKYRIZI or (866) 759-7494 if you need help. Receive training on how to inject SKYRIZI before giving injections.

Q. What should I do with both used prefilled syringes after my injections?

A. Throw away (dispose of) both used prefilled syringes in a sharps disposal container. Do not put in household trash. For more information, see “Used SKYRIZI Prefilled Syringe Disposal” section.

You can sign up to receive sharps containers for SKYRIZI prefilled syringe disposal at no additional cost by going to www.SKYRIZI.com or calling (866) 759-7494

Q. How do I know when the injection is complete?

A. The injection is complete when the prefilled syringe is empty, the plunger rod is pushed all the way in, and the syringe needle guard is activated.

Used SKYRIZI Prefilled Syringe Disposal

Throw away (dispose of) both used prefilled syringes in a sharps disposal container. Do not put in household trash.

If you do not have an FDA-cleared sharps disposal container, you may use a household container that:

- is made of a heavy-duty plastic,
- can be closed with a tight-fitting, puncture-resistant lid, without sharps being able to come out,
- stays upright and stable during use,
- is leak-resistant, and
- has been properly labeled to warn of hazardous waste inside the container.

When your sharps disposal container is almost full, you will need to follow your community guidelines for the right way to dispose of your sharps disposal container. There may be state or local laws about how you should throw away used needles and syringes.

For more information about safe sharps disposal, and for specific information about sharps disposal in the state that you live in, go to the FDA's website at: www.fda.gov/safesharpsdisposal.

Do not recycle your used sharps disposal container.

Manufactured by: AbbVie Inc., North Chicago, IL 60064, U.S.A.
US License Number 1889
SKYRIZI® is a trademark of AbbVie Biotechnology Ltd.
© 2019-2024 AbbVie Inc.
20078139

This Instructions for Use have been approved by the U.S. Food and Drug Administration.

Revised: 3/2024

Instructions for Use
SKYRIZI® (sky-RIZZ-ee)
(risankizumab-rzaa)
injection, for subcutaneous use
180 mg/1.2 mL (150 mg/mL) single-dose prefilled syringe for a total 180 mg/1.2 mL dose

Read Before First Use

Refer to the Medication Guide for product information.

SKYRIZI Single-Dose Prefilled Syringe

Keep SKYRIZI and all medicines out of the reach of children.

Important Information:

- Keep SKYRIZI in the original carton to protect from light until time to use.
- The liquid should look clear to yellow and may contain tiny white or clear particles.
- Do not use SKYRIZI if the liquid is discolored, cloudy or contains flakes or large particles. Return product to pharmacy.
- Do not use SKYRIZI if the expiration date (EXP:) shown on the carton and prefilled syringe has passed. Return product to pharmacy.
- Do not use SKYRIZI if the liquid has been frozen (even if thawed).
- Do not shake the syringe.
- Do not use SKYRIZI if the prefilled syringe has been dropped or damaged. Return product to pharmacy.
- Do not use SKYRIZI if carton perforations are broken. Return product to the pharmacy.
- Do not remove the needle cover until right before giving the injection.
- SKYRIZI is not made with natural rubber latex.

Please Read Complete Instructions for Use Before Using SKYRIZI Prefilled Syringe

Before Injecting:

- Receive training on how to inject SKYRIZI before giving injections. Call your healthcare provider or (866) SKYRIZI or (866) 759-7494 if you need help.
- Mark your calendar ahead of time to remember when to take SKYRIZI.
- Leave the carton at room temperature and out of direct sunlight for 15 to 30 minutes to warm.
  - Do not remove the syringes from the carton while allowing SKYRIZI to reach room temperature.
  - Do not warm SKYRIZI in any other way (for example, do not warm it in a microwave or in hot water).

Important Information:

- The liquid should look clear to yellow and may contain tiny white or clear particles.
- Do not use SKYRIZI if the liquid is discolored, cloudy or contains flakes or large particles. Return product to pharmacy.
- Do not use SKYRIZI if the expiration date (EXP:) shown on the carton and prefilled syringe has passed. Return product to pharmacy.
- Do not use SKYRIZI if the prefilled syringe has been dropped or damaged. Return product to pharmacy.
- Do not use SKYRIZI if carton perforations are broken. Return product to pharmacy.

Storage Information:

- Store SKYRIZI in the refrigerator between 36°F to 46°F (2°C to 8°C).
- Do not shake SKYRIZI.
- Keep SKYRIZI in the original carton to protect from light until time to use.
- SKYRIZI is not made with natural rubber latex.
- Do not use if liquid has been frozen (even if thawed).

Keep SKYRIZI and all medicines out of the reach of children.

Call your healthcare provider or (866) SKYRIZI or (866) 759-7494. if you need help or do not know how to proceed.

Gather the supplies for the injection and place the following on a clean, flat surface:

- 1 prefilled syringe
- 1 alcohol swab and 1 cotton ball or gauze pad (not included)
- FDA-cleared sharps disposal container (not included) See “Used SKYRIZI Prefilled Syringe Disposal” for information on how to throw away (dispose of) used prefilled syringes.

Wash and dry your hands.

Remove prefilled syringe from blue and white cardboard sleeve by holding the finger grip

Pick from the 3 injectable areas:

- Front of left thigh or right thigh
- Your abdomen (belly) at least 2 inches from your navel (belly button)

Wipe the injection site in a circular motion with the alcohol swab before the injection.

- Do not touch or blow on the injection site after it is cleaned. Allow the skin to dry before injecting.
- Do not inject through clothes.
- Do not inject into skin that is sore, bruised, red, hard, scarred, or has stretch marks.

Hold the prefilled syringe with covered needle facing down, as shown.
Check the liquid in the prefilled syringe.

- It is normal to see one or more bubbles in the window.
- The liquid should look clear to yellow and may contain tiny white or clear particles.
- Do not use the prefilled syringe if liquid is discolored, cloudy or contains flakes or large particles.

Remove the needle cover.

- Do not hold or pull plunger rod when removing the needle cover.
- Hold the prefilled syringe in 1 hand between the finger grip and needle cover.
- With the other hand, carefully pull the needle cover straight off.
- You may see a drop of liquid at the end of the needle. This is normal.
- Throw away the needle cover.
- Do not touch the needle with your fingers or let the needle touch anything.

Hold the body of the prefilled syringe in 1 hand between the thumb and index finger.
Gently pinch the area of cleaned skin with your other hand and hold it firmly.
Insert the needle into the skin at about a 45-degree angle using a quick, short movement. Hold angle steady.

Slowly push the plunger rod all the way in until all of the liquid is injected and the prefilled syringe is empty.
Pull the needle out of the skin while keeping the prefilled syringe at the same angle.
Release the plunger rod .

- Allow the prefilled syringe to move up until the entire needle is covered by the needle guard.

The needle guard will not automatically activate unless all the liquid has been injected.

- Press a cotton ball or gauze pad over the injection site and hold for 10 seconds.
- Do not rub the injection site. You may have slight bleeding. This is normal.

Put your used prefilled syringe in an FDA-cleared sharps disposal container right away after use.

- Do not throw away (dispose of) the used prefilled syringe in the household trash.

For more information, or if you do not have an FDA-cleared sharps container see "Used SKYRIZI Prefilled Syringe Disposal" section located on the other side of these instructions.

Questions About Using the SKYRIZI Syringe

Q. What if I have not received in-person training from a healthcare professional?

A. Call your healthcare provider or (866) SKYRIZI or (866) 759-7494 if you need help. Receive training on how to inject SKYRIZI before giving injections.

Q. What should I do with the used prefilled syringe after my injection?

A. Throw away (dispose of) the used prefilled syringe in a sharps disposal container. Do not put in household trash. For more information, see “Used SKYRIZI Prefilled Syringe Disposal” section.

You can sign up to receive sharps containers for SKYRIZI syringe disposal at no additional cost by going to www.SKYRIZI.com or calling (866) 759-7494

Q. How do I know when the injection is complete?

A. The injection is complete when the prefilled syringe is empty, the plunger rod is pushed all the way in, and the syringe needle guard is activated.

Used SKYRIZI Prefilled Syringe Disposal

Throw away (dispose of) the used prefilled syringe in a sharps disposal container. Do not put in household trash.

If you do not have an FDA-cleared sharps disposal container, you may use a household container that:

- is made of a heavy-duty plastic,
- can be closed with a tight-fitting, puncture-resistant lid, without sharps being able to come out,
- stays upright and stable during use,
- is leak-resistant, and
- has been properly labeled to warn of hazardous waste inside the container.

When your sharps disposal container is almost full, you will need to follow your community guidelines for the right way to dispose of your sharps disposal container. There may be state or local laws about how you should throw away used needles and syringes.

For more information about safe sharps disposal, and for specific information about shams disposal in the state that you live in, go to the FDA's website at: www.fda.gov/safesharpsdisposal.

Do not recycle your used sharps disposal container.

Manufactured by: AbbVie Inc., North Chicago, IL 60064, U.S.A.
US License Number 1889
SKYRIZI® is a trademark of AbbVie Biotechnology Ltd.
© 2019-2025 AbbVie Inc.
20087559

These Instructions for Use have been approved by the U.S. Food and Drug Administration.

Revised: 9/2025

Instructions for Use
SKYRIZI® (sky-RIZZ-ee)
(risankizumab-rzaa)
injection, for subcutaneous use
2 x 180 mg/1.2 mL (150 mg/mL) single-dose prefilled syringe for a total 360 mg/2.4 mL dose

Read Before First Use

Refer to the Medication Guide for product information.

SKYRIZI Single-Dose Prefilled Syringe

Keep SKYRIZI and all medicines out of the reach of children.

Important Information:

- Keep SKYRIZI in the original carton to protect from light until time to use.
- The liquid should look clear to yellow and may contain tiny white or clear particles.
- Do not use SKYRIZI if the liquid is discolored, cloudy or contains flakes or large particles. Return product to pharmacy.
- Do not use SKYRIZI if the expiration date (EXP:) shown on the carton and prefilled syringe has passed. Return product to pharmacy.
- Do not use SKYRIZI if the liquid has been frozen (even if thawed).
- Do not shake the syringe.
- Do not use SKYRIZI if the prefilled syringe has been dropped or damaged. Return product to pharmacy.
- Do not use SKYRIZI if carton perforations are broken. Return product to the pharmacy.
- Do not remove the needle cover until right before giving the injections.
- SKYRIZI is not made with natural rubber latex.

Please Read Complete Instructions for Use Before Using SKYRIZI Prefilled Syringe

Before Injecting:

- Receive training on how to inject SKYRIZI before giving injections. Call your healthcare provider or (866) SKYRIZI or (866) 759-7494 if you need help.
- Mark your calendar ahead of time to remember when to take SKYRIZI.
- Leave the carton at room temperature and out of direct sunlight for 15 to 30 minutes to warm.
  - Do not remove the syringes from the carton while allowing SKYRIZI to reach room temperature.
  - Do not warm SKYRIZI in any other way (for example, do not warm it in a microwave or in hot water).

Important Information:

- The liquid should look clear to slightly yellow and may contain tiny white or clear particles.
- Do not use SKYRIZI if the liquid is discolored, cloudy or contains flakes or large particles. Return product to pharmacy.
- Do not use SKYRIZI if the expiration date (EXP:) shown on the carton and prefilled syringe has passed. Return product to pharmacy.
- Do not use SKYRIZI if the prefilled syringe has been dropped or damaged. Return product to pharmacy.
- Do not use SKYRIZI if carton perforations are broken. Return product to pharmacy.

Storage Information:

- Store SKYRIZI in the refrigerator between 36°F to 46°F (2°C to 8°C).
- Do not shake SKYRIZI.
- Keep SKYRIZI in the original carton to protect from light until time to use.
- SKYRIZI is not made with natural rubber latex.
- Do not use if liquid has been frozen (even if thawed).

Keep SKYRIZI and all medicines out of the reach of children.

Call your healthcare provider or (866) SKYRIZI or (866) 759-7494. if you need help or do not know how to proceed.

Gather the supplies for the injections and place the following on a clean, flat surface:

- 2 prefilled syringes
- 2 alcohol swabs and 2 cotton balls or gauze pads (not included)
- FDA-cleared sharps disposal container (not included) See “Used SKYRIZI Prefilled Syringe Disposal” for information on how to throw away (dispose of) used prefilled syringes.

Wash and dry your hands.
Start with 1 prefilled syringe for first injection.

Pick from the 3 injectable areas:

- Front of left thigh or right thigh
- Your abdomen (belly) at least 2 inches from your navel (belly button)

Wipe the injection site in a circular motion with the alcohol swab (before both injections)

- Do not touch or blow on the injection site after it is cleaned. Allow the skin to dry before injecting.
- Do not inject through clothes.
- Do not inject into skin that is sore, bruised, red, hard, scarred, or has stretch marks.

Hold the prefilled syringe with covered needle facing down, as shown.
Check the liquid in the prefilled syringe.

- It is normal to see one or more bubbles in the window.
- The liquid should look clear to yellow and may contain tiny white or clear particles.
- Do not use the prefilled syringe if liquid is discolored, cloudy or contains flakes or large particles.

Remove the needle cover.

- Do not hold or pull plunger rod when removing the needle cover.
- Hold the prefilled syringe in 1 hand between the finger grip and needle cover.
- With the other hand, carefully pull the needle cover straight off.
- You may see a drop of liquid at the end of the needle. This is normal.
- Throw away the needle cover.
- Do not touch the needle with your fingers or let the needle touch anything.

Hold the body of the prefilled syringe in 1 hand between the thumb and index finger.
Gently pinch the area of cleaned skin with your other hand and hold it firmly.
Insert the needle into the skin at about a 45-degree angle using a quick, short movement. Hold angle steady.

Slowly push the plunger rod all the way in until all of the liquid is injected and the prefilled syringe is empty.
Pull the needle out of the skin while keeping the prefilled syringe at the same angle.
Release the plunger rod.

- Allow the prefilled syringe to move up until the entire needle is covered by the needle guard.

The needle guard will not automatically activate unless all the liquid has been injected.

- Press a cotton ball or gauze pad over the injection site and hold for 10 seconds.
- Do not rub the injection site. You may have slight bleeding. This is normal.

Repeat Steps 2 through 6 with the 2nd prefilled syringe for a full dose.

- Use the 2nd prefilled syringe right after using the 1st syringe.

Put your used prefilled syringes in an FDA-cleared sharps disposal container right away after use.

- Do not throw away (dispose of) used prefilled syringes in the household trash.

For more information, or if you do not have an FDA-cleared sharps container see "Used SKYRIZI Prefilled Syringe Disposal" section located on the other side of these instructions.

Questions About Using the SKYRIZI Syringe

Q. What if I have not received in-person training from a healthcare professional?

A. Call your healthcare provider or (866) SKYRIZI or (866) 759-7494 if you need help. Receive training on how to inject SKYRIZI before giving injections.

Q. What should I do with both used prefilled syringes after my injections?

A. Throw away (dispose of) both used prefilled syringes in a sharps disposal container. Do not put in household trash. For more information, see “Used SKYRIZI Prefilled Syringe Disposal” section.

You can sign up to receive sharps containers for SKYRIZI syringe disposal at no additional cost by going to www.SKYRIZI.com or calling (866) 759-7494

Q. How do I know when the injection is complete?

A. The injection is complete when the prefilled syringe is empty, the plunger rod is pushed all the way in, and the syringe needle guard is activated.

Used SKYRIZI Prefilled Syringe Disposal

Throw away (dispose of) both used prefilled syringes in a sharps disposal container. Do not put in household trash.

If you do not have an FDA-cleared sharps disposal container, you may use a household container that:

- is made of a heavy-duty plastic,
- can be closed with a tight-fitting, puncture-resistant lid, without sharps being able to come out,
- stays upright and stable during use,
- is leak-resistant, and
- has been properly labeled to warn of hazardous waste inside the container.

When your sharps disposal container is almost full, you will need to follow your community guidelines for the right way to dispose of your sharps disposal container. There may be state or local laws about how you should throw away used needles and syringes.

For more information about safe sharps disposal, and for specific information about shams disposal in the state that you live in, go to the FDA's website at: www.fda.gov/safesharpsdisposal.

Do not recycle your used sharps disposal container.

Manufactured by: AbbVie Inc., North Chicago, IL 60064, U.S.A.
US License Number 1889
SKYRIZI® is a trademark of AbbVie Biotechnology Ltd.
© 2019-2025 AbbVie Inc.
20087560

These Instructions for Use have been approved by the U.S. Food and Drug Administration.

Revised: 9/2025

Instructions for Use
SKYRIZI® (sky-RIZZ-ee)
(risankizumab-rzaa)
injection, for subcutaneous use
4 x 90 mg/mL single-dose prefilled syringes for a total 360 mg/4 mL dose

Read Before First Use

Refer to the Medication Guide for product information.

SKYRIZI Single-Dose Prefilled Syringe

Keep SKYRIZI and all medicines out of the reach of children.

Important Information:

- Keep SKYRIZI in the original carton to protect from light until time to use.
- The liquid should look clear to slightly yellow and may contain tiny white or clear particles.
- Do not use SKYRIZI if the liquid is discolored, cloudy or contains flakes or large particles. Return product to pharmacy.
- Do not use SKYRIZI if the expiration date (EXP:) shown on the carton and prefilled syringe has passed. Return product to pharmacy.
- Do not use SKYRIZI if the liquid has been frozen (even if thawed).
- Do not shake the syringe.
- Do not use SKYRIZI if the prefilled syringe has been dropped or damaged. Return product to pharmacy.
- Do not use SKYRIZI if carton perforations are broken. Return product to the pharmacy.
- Do not remove the needle cover until right before giving the injections.
- SKYRIZI is not made with natural rubber latex.

Please Read Complete Instructions for Use Before Using SKYRIZI Prefilled Syringe

Before Injecting:

- Receive training on how to inject SKYRIZI before giving injections. Call your healthcare provider or (866) SKYRIZI or (866) 759-7494 if you need help.
- Mark your calendar ahead of time to remember when to take SKYRIZI.
- Leave the carton at room temperature and out of direct sunlight for 15 to 30 minutes to warm.
  - Do not remove the prefilled syringes from the carton while allowing SKYRIZI to reach room temperature.
  - Do not warm SKYRIZI in any other way (for example, do not warm it in a microwave or in hot water).

Important Information:

- The liquid should look clear to slightly yellow and may contain tiny white or clear particles.
- Do not use SKYRIZI if the liquid is discolored, cloudy or contains flakes or large particles. Return product to pharmacy.
- Do not use SKYRIZI if the expiration date (EXP:) shown on the carton and prefilled syringe has passed. Return product to pharmacy.
- Do not use SKYRIZI if the prefilled syringe has been dropped or damaged. Return product to pharmacy.
- Do not use SKYRIZI if carton perforations are broken. Return product to pharmacy.

Storage Information:

- Store SKYRIZI in the refrigerator between 36°F to 46°F (2°C to 8°C).
- Do not shake SKYRIZI.
- Keep SKYRIZI in the original carton to protect from light until time to use.
- SKYRIZI is not made with natural rubber latex.
- Do not use if liquid has been frozen (even if thawed).

Keep SKYRIZI and all medicines out of the reach of children.

Call your healthcare provider or (866) SKYRIZI or (866) 759-7494 if you need help or do not know how to proceed.

Gather the supplies for the injections and place the following on a clean, flat surface:

- 4 prefilled syringes
- 4 alcohol swabs and 4 cotton balls or gauze pads (not included)
- FDA-cleared sharps disposal container (not included) See “Used SKYRIZI Prefilled Syringe Disposal” for information on how to throw away (dispose of) used prefilled syringes.

Wash and dry your hands.
Start with 1 prefilled syringe for first injection.

Pick from the 3 injectable areas:

- Front of left thigh or right thigh
- Your abdomen (belly) at least 2 inches from your navel (belly button)

Wipe the injection site in a circular motion with the alcohol swab (before all four injections)

- Do not touch or blow on the injection site after it is cleaned. Allow the skin to dry before injecting.
- Do not inject through clothes.
- Do not inject into skin that is sore, bruised, red, hard, scarred, or has stretch marks.

Hold the prefilled syringe with covered needle facing down, as shown.
Check the liquid in the prefilled syringe.

- It is normal to see one or more bubbles in the window.
- The liquid should look clear to slightly yellow and may contain tiny white or clear particles.
- Do not use the prefilled syringe if liquid is discolored, cloudy or contains flakes or large particles.

Remove the needle cover.

- Do not hold or pull plunger rod when removing the needle cover.
- Hold the syringe in 1 hand between the finger grip and needle cover.
- With the other hand, carefully pull the needle cover straight off.
- You may see a drop of liquid at the end of the needle. This is normal.
- Throw away the needle cover.
- Do not touch the needle with your fingers or let the needle touch anything.

Hold the body of the prefilled syringe in 1 hand between the thumb and index finger.
Gently pinch the area of cleaned skin with your other hand and hold it firmly.
Insert the needle into the skin at about a 45-degree angle using a quick, short movement. Hold angle steady.

Slowly push the plunger rod all the way in until all of the liquid is injected and the syringe is empty.
Pull the needle out of the skin while keeping the syringe at the same angle.
Release the plunger rod.

- Allow the prefilled syringe to move up until the entire needle is covered by the needle guard.

The needle guard will not automatically activate unless all the liquid has been injected.

- Press a cotton ball or gauze pad over the injection site and hold for 10 seconds.
- Do not rub the injection site. You may have slight bleeding. This is normal.

Repeat Steps 2 through 6 with the 2nd, 3rd, and 4th prefilled syringe for a full dose.

- Use the 2nd, 3rd, and 4th prefilled syringe right after using the 1st syringe.

Put your used prefilled syringes in an FDA-cleared sharps disposal container right away after use.

- Do not throw away (dispose of) used prefilled syringes in the household trash.

For more information, or if you do not have an FDA-cleared sharps container see “Used SKYRIZI Prefilled Syringe Disposal” section located on the other side of these instructions.

Questions About Using the SKYRIZI Syringe

Q. What if I have not received in-person training from a healthcare professional?

A. Call your healthcare provider or (866) SKYRIZI or (866) 759-7494 if you need help. Receive training on how to inject SKYRIZI before giving injections.

Q. What should I do with all four used prefilled syringes after my injections?

A. Throw away (dispose of) all 4 used prefilled syringes in a sharps disposal container. Do not put in household trash. For more information, see “Used SKYRIZI Prefilled Syringe Disposal” section.

You can sign up to receive sharps containers for SKYRIZI prefilled syringe disposal at no additional cost by going to www.SKYRIZI.com or calling (866) 759-7494

Q. How do I know when the injection is complete?

A. The injection is complete when the prefilled syringe is empty, the plunger rod is pushed all the way in, and the syringe needle guard is activated.

Used SKYRIZI Prefilled Syringe Disposal

Throw away (dispose of) all four used prefilled syringes in a sharps disposal container. Do not put in household trash.

If you do not have an FDA-cleared sharps disposal container, you may use a household container that:

- is made of a heavy-duty plastic,
- can be closed with a tight-fitting, puncture-resistant lid, without sharps being able to come out,
- stays upright and stable during use,
- is leak-resistant, and
- has been properly labeled to warn of hazardous waste inside the container.

When your sharps disposal container is almost full, you will need to follow your community guidelines for the right way to dispose of your sharps disposal container. There may be state or local laws about how you should throw away used needles and syringes.

For more information about safe sharps disposal, and for specific information about sharps disposal in the state that you live in, go to the FDA's website at: www.fda.gov/safesharpsdisposal.

Do not recycle your used sharps disposal container.

Manufactured by: AbbVie Inc., North Chicago, IL 60064, U.S.A.
US License Number 1889
SKYRIZI® is a trademark of AbbVie Biotechnology Ltd.
© 2019-2024 AbbVie Inc.

This Instructions for Use have been approved by the U.S. Food and Drug Administration.

Revised: 3/2024

Instructions for Use
SKYRIZI® (sky-RIZZ-ee) On-Body Injector
risankizumab-rzaa

injection, for subcutaneous use only

On-Body Injector and 180 mg/1.2 mL Prefilled Cartridge,
On-Body Injector and 360 mg/2.4 mL Prefilled Cartridge

Read this Instructions for Use before you start using SKYRIZI and each time you get a refill. There may be new information. This information does not take the place of talking to your healthcare provider about your medical condition or treatment.

Refer to the Medication Guide for SKYRIZI product information. Call your healthcare provider, call (866) SKYRIZI or (866) 759-7494 or go to SKYRIZI.com if you need help.

Important information you need to know before injecting SKYRIZI

- Receive training on how to inject SKYRIZI before giving an injection.
- Do not shake the SKYRIZI carton, On-Body Injector or prefilled cartridge.
- Do not remove the On-Body Injector or prefilled cartridge from the carton until you are ready to inject.
- Do not wait more than 5 minutes to start the injection after loading the cleaned prefilled cartridge into the On-Body Injector. Waiting will dry out the medicine and the On-Body Injector will not work afterwards.
- Do not touch the start button until you place the On-Body Injector loaded with the prefilled cartridge onto your skin and are ready to inject.
  ◦ You can only press the start button 1-time.
- Do not use On-Body Injector or prefilled cartridge if either has been dropped or damaged.
- Do not reuse On-Body Injector or prefilled cartridge. The On-Body Injector and prefilled cartridge are for 1-time (single-dose) use only.
- Do not let the On-Body Injector get wet with water or any other liquids.
- This single-dose On-Body Injector is designed for use with SKYRIZI prefilled cartridge only.
- Physical activity should be limited during the injection process. Moderate physical activities can be done, such as walking, reaching and bending.
- Do not use SKYRIZI if the expiration date (EXP:) has passed.
- Do not use the prefilled cartridge if the liquid is discolored, cloudy or contains flakes or large particles. The liquid should look clear to yellow and may contain tiny white or clear particles.
- The On-Body Injector and the prefilled cartridge are not made with natural rubber latex.
- Keep SKYRIZI and all medicines out of the reach of children.

Storage and preparation for use

- Keep SKYRIZI in the original carton to protect from light and physical damage until time to use.
- Store SKYRIZI in your refrigerator between 36°F to 46°F (2°C to 8°C).
- When ready to use, take the carton out of the refrigerator and leave it at room temperature for at least 45 minutes up to 90 minutes to allow SKYRIZI to warm.
  - The On-Body Injector will not work if left at room temperature for less than 45 minutes.
- Do not leave out in direct sunlight.
- Do not remove the On-body Injector or prefilled cartridge from the carton while allowing SKYRIZI to reach room temperature.
- Do not warm SKYRIZI in any other way. For example, do not warm it in a microwave or in hot water.
- Do not use if liquid has been frozen (even if thawed).
- Do not use SKYRIZI if carton perforations are broken. Return product to the pharmacy.
- Do not use the On-Body Injector and prefilled cartridge if the white paper tray seal is missing or damaged and return the carton to the pharmacy.

Get to know your SKYRIZI On-Body Injector and prefilled cartridge

Please read complete Instructions for Use before using SKYRIZI. Call your healthcare provider or (866) SKYRIZI or (866) 759-7494 or go to www.SKYRIZI.com if you need help or if you do not know how to proceed.

Step 1 Get ready

Before using SKYRIZI, you should receive training on how to inject SKYRIZI.

Check expiration date

- Remove the carton from the refrigerator.
- Check expiration date (EXP:) on the carton.
- Do not use SKYRIZI if the expiration date (EXP:) has passed.

Wait at least 45 minutes

- Leave unopened carton at room temperature to warm.
- Keep out of direct sunlight.
- Wait at least 45 minutes up to a maximum of 90 minutes to allow SKYRIZI to warm.
  - The On-Body Injector will not work if left at room temperature for less than 45 minutes.
- Do not warm SKYRIZI in any other way (for example, do not warm it in a microwave or in hot water).

Open the carton and remove the plastic tray

- Lift up the flap on the side of the carton.
- Take out the plastic tray.

Gather all supplies and wash hands

- Place the following on a clean surface:
  ◦ plastic tray containing the On-Body Injector and prefilled cartridge (included)
  ◦ 2 alcohol wipes (not included)
  ◦ cotton ball or gauze pad (not included)
  ◦ sharps disposal container (not included) (see “Disposing of SKYRIZI”)
- Wash and dry your hands.

Remove the white paper tray seal

- Locate the black arrow.
- Peel away the white paper tray seal from the plastic tray.
- Do not use the On-Body Injector and prefilled cartridge if the white paper tray seal is missing or damaged and return the carton to the pharmacy.

Lift the plastic cover

- Locate the rounded opening on the top cover.
- Insert your pointer finger in the opening and place your thumb on the opposite side.
- Lift the cover to remove and set aside.

Inspect the On-Body Injector

- Check that the On-Body Injector is intact and undamaged.
- Do not close the gray door before the prefilled cartridge is loaded.
- The gray door should be slightly open.
- If the gray door does not open, press in firmly on the gray door ridges (left side of door) and swing open the door.
- Do not use On-Body Injector if you drop it, discover missing pieces, or it is damaged.
- Do not let the On-Body Injector get wet with water or any other liquids.

Do not touch the gray start button until it is time to inject. It can be pressed 1-time only.
If the gray start button is pressed before placing it on your body, the On-Body Injector can no longer be used. Call (866) SKYRIZI or (866) 759-7494.

- Do not touch the needle cover or the needle.
- Proceed to Set up On-Body Injector.

Step 2 Set up On-Body Injector

Fully open the gray door
Avoid touching the needle cover or the needle on the back of the On-Body Injector. The needle is behind the needle cover.

- Swing the gray door all the way to the right to open it.
- If the gray door does not open, press in firmly on the gray door ridges (left side of door) and swing open the door.
- Do not close the gray door before the prefilled cartridge is loaded.
- Do not touch the needle cover or needle.
- Put the On-Body Injector aside.

Inspect the prefilled cartridge

- Carefully remove the prefilled cartridge from the plastic tray.
- Do not twist or remove cartridge top.
- Check the prefilled cartridge to make sure:
  ◦ The expiration date (EXP:) has not passed.
  ◦ The liquid should look clear to yellow and may contain tiny white or clear particles. It is normal to see one or more bubbles.
  ◦ The prefilled cartridge parts appear intact, and the clear plastic is not cracked or broken.
- Do not use if the expiration date (EXP:) has passed.
- Do not use if the liquid is cloudy, discolored, or contains flakes or large particles.
- Do not use if the liquid has been frozen (even if thawed).
- Do not use the prefilled cartridge if you drop it, discover missing pieces, or it is damaged.

Clean the smaller bottom tip of the prefilled cartridge

- Locate the smaller bottom tip of the prefilled cartridge.
- Clean the smaller bottom tip of the prefilled cartridge with an alcohol wipe. Make sure to use the alcohol wipe to clean the center of the smaller bottom tip of the prefilled cartridge.
- Do not touch the smaller bottom tip of the prefilled cartridge after cleaning.

Load the cleaned prefilled cartridge into the On-Body Injector

- Do not twist or remove the prefilled cartridge top.
- Insert the smaller bottom tip of the prefilled cartridge into the On-Body Injector first.
- Firmly push down on the prefilled cartridge top until you hear a “click”.
- After loading the prefilled cartridge, you may see a few drops of medicine on the back of the On-Body Injector. This is normal.

Make sure that you start the injection within 5 minutes after inserting the prefilled cartridge into the On-Body Injector. Waiting will dry out the medicine and the On-Body Injector will not work afterwards.

Close the gray door

- Swing the gray door to the left, then squeeze firmly and listen for the gray door to "snap" shut.
- The gray door should stay locked after loading the prefilled cartridge.
- Do not close the gray door if the prefilled cartridge is not fully inserted or is missing.
- Proceed without delay to Prepare to inject

Step 3 Prepare to inject

Keep electronic devices including cell phones at least 12 inches (30 cm) from On-Body Injector until injection is complete

Pick your injection area
Locate a firm and flat area on your bare skin. Make sure the area is clear of clothing:

- Your abdomen (belly) at least 2 inches from your navel (belly button).
- The front of your left thigh or your right thigh.
- Do not inject into areas of the skin that naturally fold or bulge because the On-Body Injector could fall off during wear.
- Do not inject into skin that is sore, bruised, red, hard, scarred, or has stretch marks, moles or excessive hair. You can trim the excessive hair from the injection area.

Clean the injection area

- Clean injection area with an alcohol wipe.
- Allow the injection area to completely dry.
- Do not touch cleaned injection area before placing the On-Body Injector on the skin.

Peel both tabs to expose adhesive

- Turn the On-Body Injector over to find both green pull tabs.

Avoid touching the needle cover (needle inside).

- Peel away the large section using the green pull tab to expose the adhesive.
- Peel away the small section using the green pull tab to expose the adhesive. This will remove the clear plastic strip, activating the On-Body Injector.
- Do not pull the adhesive material off the On-Body Injector or allow the sticky side to fold and stick to itself.
- Check the status light when the On-Body Injector beeps.
- The status light will flash blue when the On-Body Injector is activated.
- If the status light does not flash blue, call (866) SKYRIZI or (866) 759-7494.
- Do not press the gray start button yet.
- Do not touch the needle cover or the needle.

Prepare the On-Body Injector for placement

- For the abdomen (belly), move and hold the skin to create a firm, flat surface for injection at least 2 inches from your navel (belly button). Make sure to adjust your posture (sit up straight) to avoid skin folds and bulges.
- You do not need to pull the skin flat for the front of left thigh or right thigh.
- Make sure to position the On-Body Injector so that you can see the blue status light.

Place the On-Body Injector on your skin

- When the blue light flashes, the On-Body Injector is ready. Place the On-Body Injector onto the cleaned skin with the status light visible.
- Do not place the On-Body Injector on clothes. Only place on bare skin.
- Run your finger around the adhesive material to secure it. Make sure all of the adhesive is attached to your skin.
- Do not move or adjust the On-Body Injector after it has been placed on your skin.
- When the On-Body Injector is on your skin, proceed to Inject medicine

Step 4 Inject medicine

Start injection

- Firmly press the gray start button until you hear a click. Then release the gray start button.
- Do not touch the gray start button until you place the On-Body Injector loaded with the prefilled cartridge onto your skin and are ready to inject. You can only press the start button 1 time.
- You may feel a needle pinch.
- Check the status light when the On-Body Injector beeps.
- After starting the injection, the status light will continuously flash green.
- You will hear pumping sounds as the On-Body Injector delivers the medicine.
- Do not continue to use the On-Body Injector if status light flashes red and beeps. Carefully remove from skin if the status light flashes red. Call (866) SKYRIZI or (866) 759-7494.

Wait for the injection to finish

- It may take up to 5 minutes to complete full dose of medicine. The On-Body Injector will automatically stop when the injection is finished.

During the injection:
◦ the status light will continue to flash green.
◦ you will hear pumping sounds as the On-Body Injector continues delivering the medicine.
◦ moderate physical activities can be done, such as walking, reaching and bending.

- Do not continue to use the On-Body Injector if the status light flashes red and beeps. Carefully remove it from the skin if the status light flashes red and beeps. Call (866) SKYRIZI or (866) 759-7494.

Injection is finished

- The On-Body Injector will stop on its own.
- After the injection is finished, you will hear beeps and the status light will change to solid green. Check the status light. If it has changed to solid green, this means that the injection is finished.
- When the injection is finished, proceed to next step.

Remove the On-Body Injector

- Do not put your fingers on the back side of the On-Body Injector when removing it from your skin.
- When the injection is done, grab the corner of the adhesive to carefully peel the On-Body Injector from the skin.

Avoid touching the needle cover or needle on the back of the On-Body Injector.

- After removing the On-Body Injector, you will hear several beeps and the status light will turn off.
- The needle cover will cover the needle when the On-Body Injector is removed from the skin.
- It is normal to see a few small drops of liquid on your skin after removing the On-Body Injector. If you see more than a few small drops of liquid left on your skin, call (866) SKYRIZI or (866) 759-7494.
- Press a cotton ball or gauze pad over the injection site on your skin and hold for 10 seconds.
- Do not rub the injection site.
- Slight bleeding at the injection site is normal.
- Proceed to Confirm and dispose

Step 5 Confirm and dispose

Check the On-Body Injector

- Inspect the medicine window and status light.
- Check to see that the used white plunger fills the medicine window and the solid green light turns off, letting you know that all the medicine has been injected.

If the used white plunger does not fill the window, call (866) SKYRIZI or (866) 759-7494.

Put the used On-Body Injector in an FDA-cleared sharps disposal container right away after use

- Leave the prefilled cartridge in the On-Body Injector.
- Do not throw away (dispose of) the used On-Body Injector in your household trash.
- For more information, see “Disposing of SKYRIZI” section.

Please read complete Instructions for Use before using SKYRIZI. Call your healthcare provider or (866) SKYRIZI or (866) 759-7494 or go to www.SKYRIZI.com if you need help or if you do not know how to proceed.

Commonly asked questions

Q. What if I cannot open the On-Body Injector door to insert the prefilled cartridge?

A. To open the On-Body Injector door, press in firmly on the left side of the door to release the door latch. If you are still unable to open the door, call (866) SKYRIZI or (866) 759-7494.

Q. What if I push the gray start button before I place the On-Body Injector on my skin?

A. The gray start button may be pressed just 1 time only. If the gray start button is pressed before placing it on your body, it can no longer be used. Call (866) SKYRIZI or (866) 759-7494.

Q. What if the On-Body Injector does not beep and the blue status light does not flash when I remove the green pull tabs?

A. Peeling off small green pull tab will remove the clear plastic strip, activating the On-Body Injector. If all of the adhesive paper has been removed and the On-Body Injector still does not turn on, call (866) SKYRIZI or (866) 759-7494.

Q. What if I push the start button as instructed after placing the On-Body Injector on the skin and the light remains blue?

A. Firmly press the gray start button again. If the status light remains blue or flashes red, remove the On-Body Injector by carefully peeling it away from your skin. Do not re-apply the On-Body Injector. Call (866) SKYRIZI or (866) 759-7494.

Q. What if the status light flashes red and beeps while wearing the On-Body Injector?

A. If the status light continuously flashes red and beeps, do not use the On-Body Injector. If it is attached to your body, carefully remove it. Call (866) SKYRIZI or (866) 759-7494.

Q. What should I do if the On-Body Injector comes off my body during the injection?

A. The loaded On-Body Injector can no longer be used. Do not re-apply it to your body. Call (866) SKYRIZI or (866) 759-7494.

Q. How do I know when the injection is complete?

A. The injection is complete when the On-Body Injector beeps, the white plunger has completely filled the medicine window, and the status light turns from flashing green to solid green.

Q. What should I do if there are more than a few drops of liquid on the injection area?

A. Call (866) SKYRIZI or (866) 759-7494 for help.

Q. What should I do with the used On-Body Injector after my injection?

A. Throw away (dispose of) used On-Body Injector in a FDA-cleared sharps disposal container and not your household trash. You can receive a sharps container for SKYRIZI disposal at no additional cost by going to www.SKYRIZI.com or by calling (866) SKYRIZI or (866) 759-7494.

Q. What if I have not received in-person training from a healthcare professional?

A. Call your healthcare provider or (866) SKYRIZI or (866) 759-7494 if you need help.

Receive training on how to inject SKYRIZI before giving injections.

Disposing of SKYRIZI

- Put SKYRIZI in an FDA-cleared sharps disposal container right away after use. Do not throw away (dispose of) SKYRIZI in your household trash.
- If you do not have an FDA-cleared sharps disposal container, you may use a household container that is:
  ◦ made of a heavy-duty plastic,
  ◦ can be closed with a tight-fitting, puncture-resistant lid, without sharps being able to come out,
  ◦ upright and stable during use,
  ◦ leak-resistant, and
  ◦ properly labeled to warn of hazardous waste inside the container.

When your sharps disposal container is almost full, you will need to follow your community guidelines for the right way to dispose of your sharps disposal container. There may be state or local laws about how you should throw away used needles and syringes.

For more information about safe sharps disposal in the state that you live in, go to the FDA’s website at: www.fda.gov/safesharpsdisposal.

Do not recycle your used sharps disposal container.

Additional information

● Type BF applied part.

● On-Body Injector sterilized using ethylene oxide.

● Altitude range is -1,312 feet to 10,499 feet (-400 meters to 3,200 meters).

Electromagnetic Compatibility (EMC) of the On-Body Injector

The On-Body Injector is intended for home use or use in a professional healthcare environment and complies with ISO 11608-1:2014 and IEC 60601-1-2:2014.

Care should be taken to use the On-Body Injector within the following specific limits and environments to avoid adversely impacting the performance (missed or incomplete SKYRIZI dose).

- Keep electronic devices including cell phones at least 12 inches (30 cm) from the On-Body Injector until injection is complete. The potential impact of electronic interference is unknown when the On-Body Injector is operated within 12 inches (30 cm).
- Do not expose the On-Body Injector to Magnetic Resonance (MR) Environment (e.g., MRI).
- If it is used adjacent to other electrical equipment, observe the On-Body Injector and other equipment to ensure it is operating normally.

Emissions

Emissions test name | Test levels
Radiated Radio frequency electromagnetic fields | Per CISPR 11, class B

Electromagnetic Immunity

Test Name | Test Levels
Electrostatic discharge (ESD) | ± 8 kV contact ± 2 kV, ± 4 kV, ± 8 kV, ± 15 kV air
Radio frequency electromagnetic field | 10 V/m 80 MHz – 2.7 GHz
Power frequency 50 Hz magnetic field | 30 A/m

The enclosure port immunity to RF wireless communications equipment complies with IEC 60601-1-2:2014.

Glossary of symbols

Symbol

Description of Symbol

Keep dry

Sterilized using ethylene oxide

Do not re-use

Do not use if package is damaged and consult instructions for use

Date of manufacture

Batch code

Catalogue number

Serial number

Refer to instruction manual / booklet

Type BF Applied Part

MR Unsafe

Manufactured by:
AbbVie Inc., North Chicago, IL 60064, U.S.A.
US License Number 1889
SKYRIZI® is a registered trademark of AbbVie Biotechnology Ltd.
©2024 AbbVie Inc.
This Instructions for Use has been approved by the U.S. Food and Drug Administration.

Revised: 6/2024

20086115

PACKAGE LABEL

NDC 0074-2100-01

One 1 mL Single-Dose Prefilled Pen

Skyrizi® PEN 150 mg/mL

risankizumab-rzaa Injection

FOR SUBCUTANEOUS USE ONLY

Return to pharmacy if carton perforations are broken.

ATTENTION PHARMACIST:

Each patient is required to receive

the enclosed Medication Guide.

This entire carton is dispensed as a unit.

AREA FOR PHARMACY LABEL

www.SKYRIZI.com

Rx only

abbvie

PACKAGE LABEL

NDC 0074-1050-01

One 1 mL Single-Dose Prefilled Syringe

Skyrizi® 150 mg/mL

risankizumab-rzaa

injection

FOR SUBCUTANEOUS USE ONLY

Return to pharmacy if carton perforations are broken.

This entire carton is dispensed as a unit.

AREA FOR PHARMACY LABEL

www.SKYRIZI.com

Rx only

Abbvie

PACKAGE LABEL

NDC 0074-1070-01

1 x 2.4 mL Prefilled Cartridge

1 On-Body Injector

Skyrizi®

risankizumab-rzaa Injection

360 mg/2.4 mL

(150 mg/mL)

FOR SUBCUTANEOUS USE ONLY

Single-Dose

SKYRIZI.com

Rx only

abbvie

PACKAGE LABEL

NDC 0074-5015-01

Skyrizi®

risankizumab-rzaa Injection

600 mg/10 mL

(60 mg/mL)

FOR INTRAVENOUS USE ONLY

Must be diluted prior to use

One 10 mL Single-Dose Vial-

Discard Unused Portion

ATTENTION: Dispense the enclosed Medication Guide to each patient.

Rx only

abbvie

PACKAGE LABEL

NDC 0074-1069-01

Skyrizi®

risankizumab-rzaa

Injection

360 mg/2.4 mL

(150 mg/mL)

FOR SUBCUTANEOUS USE ONLY

Single-Dose

Rx Only

PACKAGE LABEL

NDC 0074-1069-02

NOT FOR SALE

Skyrizi®

risankizumab-rzaa

Injection

360 mg/2.4 mL

(150 mg/mL)

FOR SUBCUTANEOUS USE ONLY

Single-Dose

Rx Only

PACKAGE LABEL

NDC 0074-1065-01

1 x 1.2 mL Prefilled Cartridge

1 On-Body Injector

Skyrizi®

risankizumab-rzaa Injection

180 mg/1.2 mL

(150 mg/mL)

FOR SUBCUTANEOUS USE ONLY

Single-Dose

SKYRIZI.com

Rx only

abbvie

PACKAGE LABEL

NDC 0074-1066-01

Skyrizi®

risankizumab-rzaa

Injection

180 mg/1.2 mL

(150 mg/mL)

FOR SUBCUTANEOUS USE ONLY

Single-Dose

Rx Only

PACKAGE LABEL

NDC 0074-1066-02

NOT FOR SALE

Skyrizi®

risankizumab-rzaa

Injection

180 mg/1.2 mL

(150 mg/mL)

FOR SUBCUTANEOUS USE ONLY

Single-Dose

Rx Only

PACKAGE LABEL

NDC 0074-7034-02

2 x 1 mL Prefilled Syringes

Skyrizi®

risankizumab-rzaa Injection

90 mg/mL per syringe

2 x 90 mg/mL. Single-Dose Prefilled

Syringes for a total 180 mg/2 mL dose

FOR SUBCUTANEOUS USE ONLY

FOR HEALTHCARE PROVIDER ADMINISTRATION ONLY

www. SKYRIZI.com

Rx Only

abbvie

PACKAGE LABEL

NDC 0074-7032-90

One 1 mL Single-Dose Prefilled Syringe

Skyrizi®

risankizumab-rzaa Injection

90 mg/mL

FOR SUBCUTANEOUS USE ONLY

FOR HEALTHCARE PROVIDER ADMINISTRATION ONLY

www. SKYRIZI.com

Rx Only

abbvie

PACKAGE LABEL

NDC 0074-7036-04

4 x 1 mL Prefilled Syringes

Skyrizi®

risankizumab-rzaa Injection

90 mg/mL per syringe

4 x 90 mg/mL Single-Dose Prefilled

Syringes for a total 360 mg/4 mL dose

FOR SUBCUTANEOUS USE ONLY

FOR HEALTHCARE PROVIDER ADMINISTRATION ONLY

ATTENTION PHARMACIST:

Each patient is required to receive the enclosed Medication Guide.

The entire carton is to be dispensed as a unit.

Return to Pharmacy if carton seal is broken or missing.

www. SKYRIZI.com

Rx Only

Abbvie

PACKAGE LABEL

NDC 0074-7032-01

Skyrizi® 90 mg/mL

risankizumab-rzaa

Injection

For Subcutaneous Use Only

FOR HEALTHCARE PROVIDER ADMINISTRATION ONLY

FOR A 350 MG DOES,

FOUR 90 MG SYRINGES ARE REQUIRED,

INJECT ALL 4 SYRINGES FOR A FULL DOSE

www.SKYRIZI.com

Rx Only

abbvie

PACKAGE LABEL

NDC 0074-7040-02

2 x 90 mg/mL Single Dose Prefilled Syringes

Skyrizi®

90 mg/mL per syringe

2 x 90 mg/mL Single-Dose Prefilled

Syringes for a total 180 mg/2 mL dose

risankizumab-rzaa
Injection

FOR SUBCUTANEOUS USE ONLY

Return to pharmacy if carton
perforations are broken.

ATTENTION PHARMACIST:

Each patient is required to receive
the enclosed Medication Guide.

This entire carton is to be
dispensed as a unit.

FOR A 180 MG DOSE,
TWO 90 MG SYRINGES ARE REQUIRED.
INJECT 2 SYRINGES FOR A FULL DOSE.

www.skyrizi.com

Rx only

abbvie

PACKAGE LABEL

NDC 0074-7042-04

4 x 90 mg/mL Single Dose Prefilled Syringes

Skyrizi®

90 mg/mL per syringe

4 x 90 mg/mL Single-Dose Prefilled
Syringes for a total 360 mg/4 mL dose

risankizumab-rzaa
Injection

FOR SUBCUTANEOUS USE ONLY

Return to pharmacy if carton perforations are broken.

ATTENTION PHARMACIST:

Each patient is required to receive the
enclosed Medication Guide.

This entire carton is to be dispensed as a unit.

FOR A 360 MG DOSE,
FOUR 90 MG SYRINGES ARE REQUIRED.
INJECT ALL 4 SYRINGES FOR A FULL DOSE.

www.Skyrizi.com

Rx only

abbvie

NDC 0074-8300-01

Skyrizi Prefilled Syringe, 180 mg/1.2 mL (150 mg/mL) single-dose

Carton of One (1)

NDC 0074-8350-01

Skyrizi Prefilled Syringe, 180 mg/1.2 mL (150 mg/mL) single-dose

Carton of Two (2)